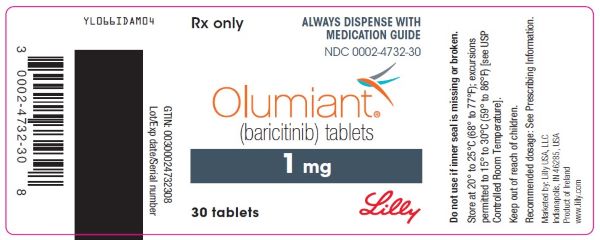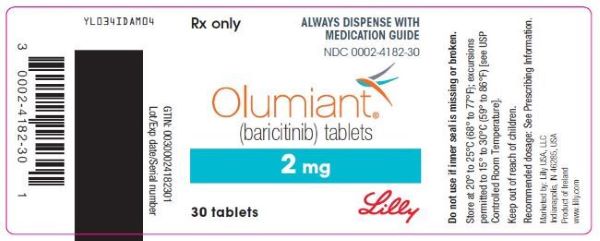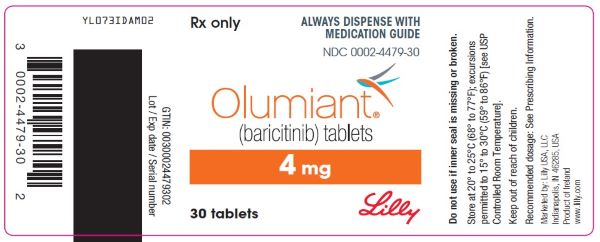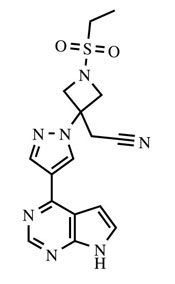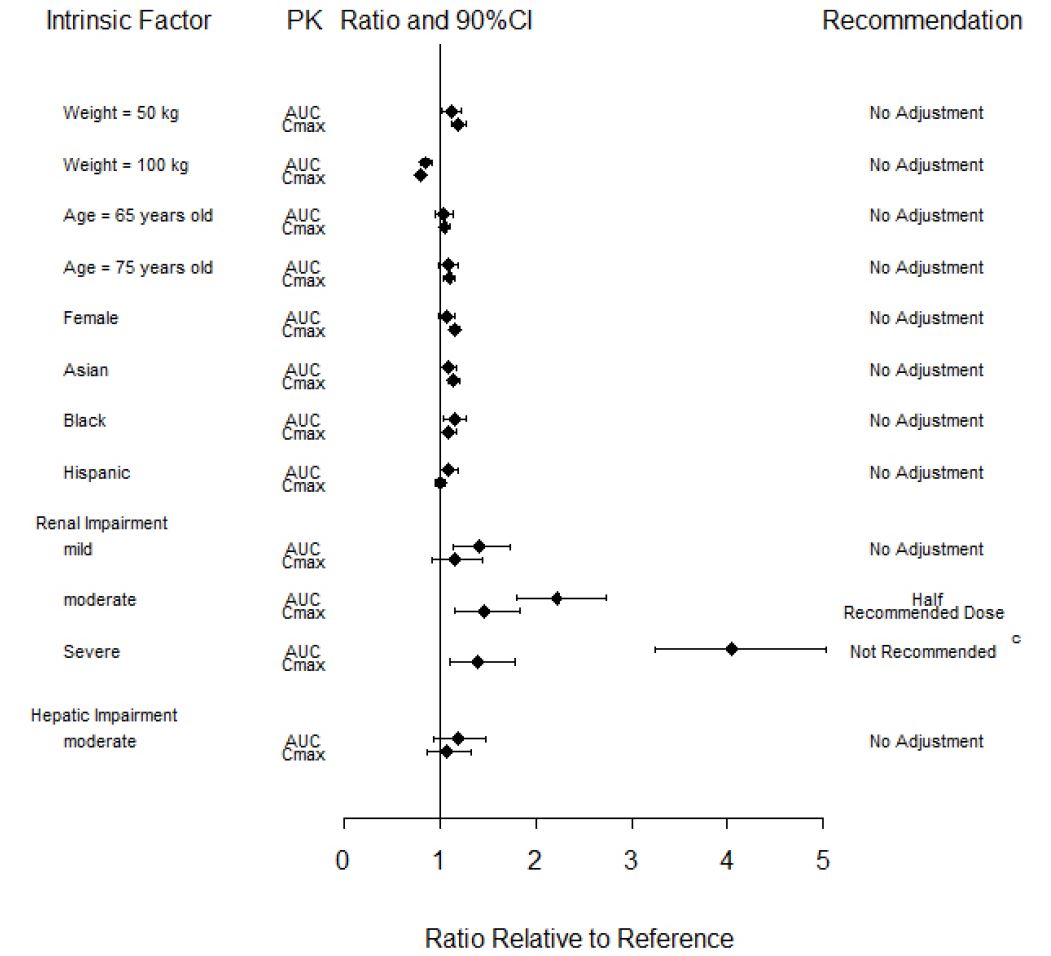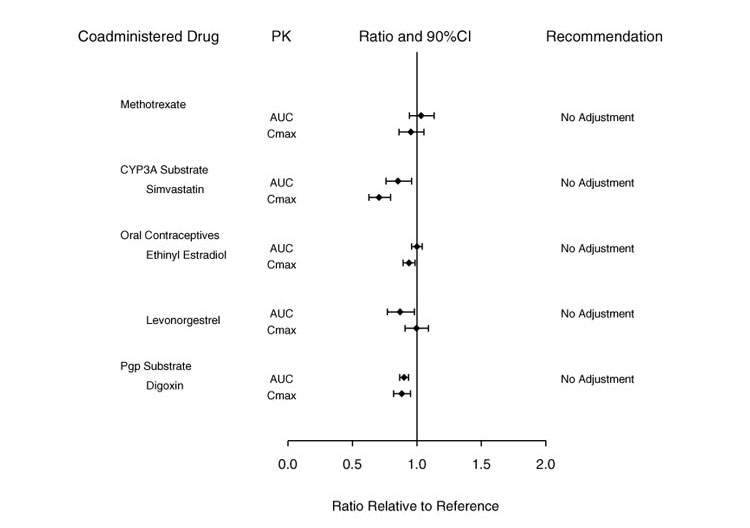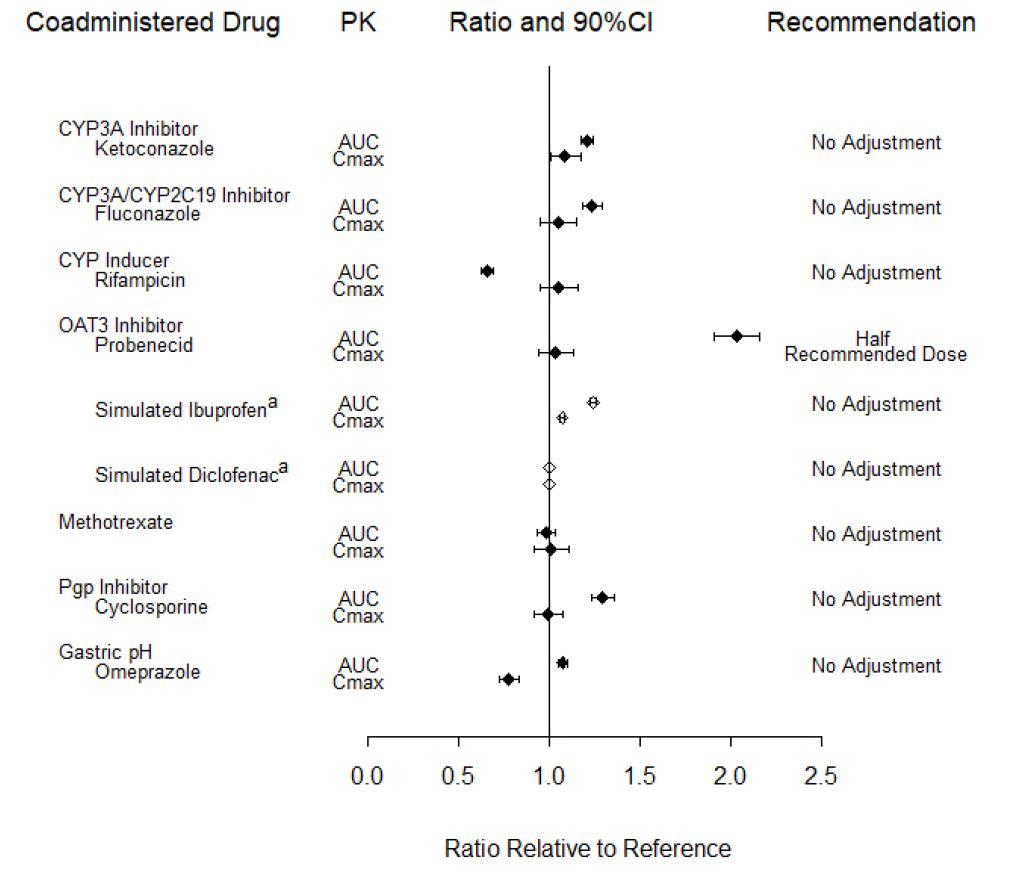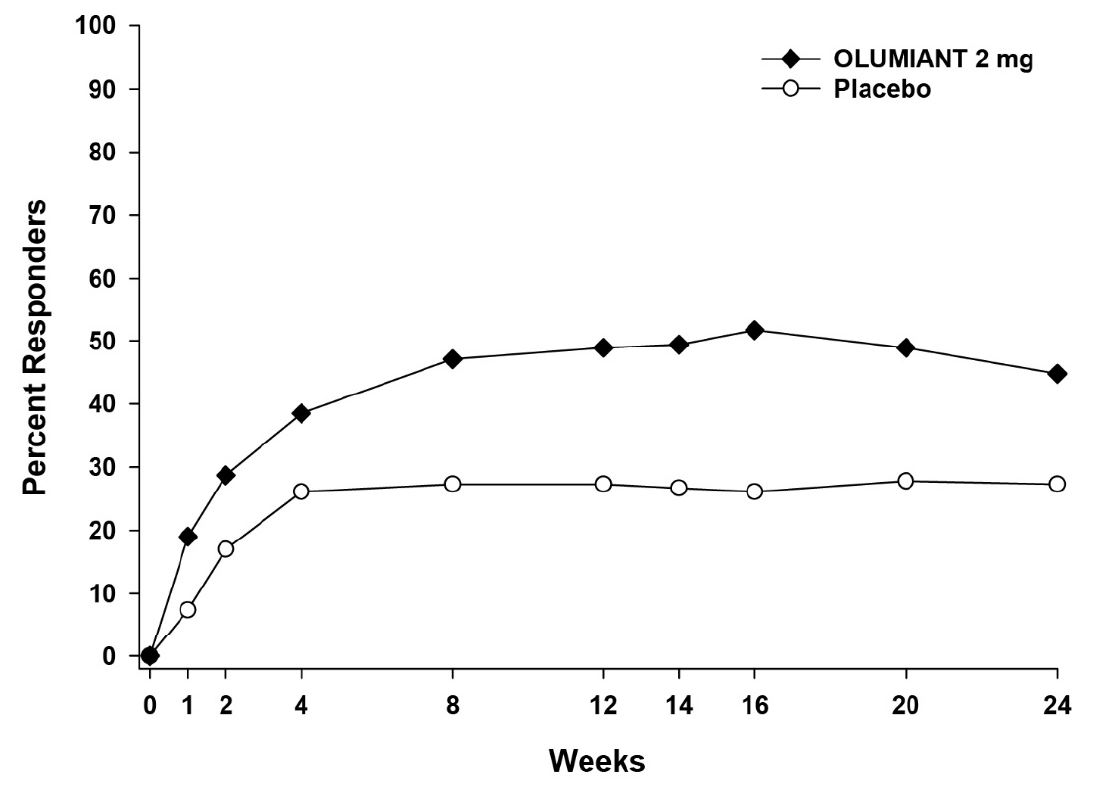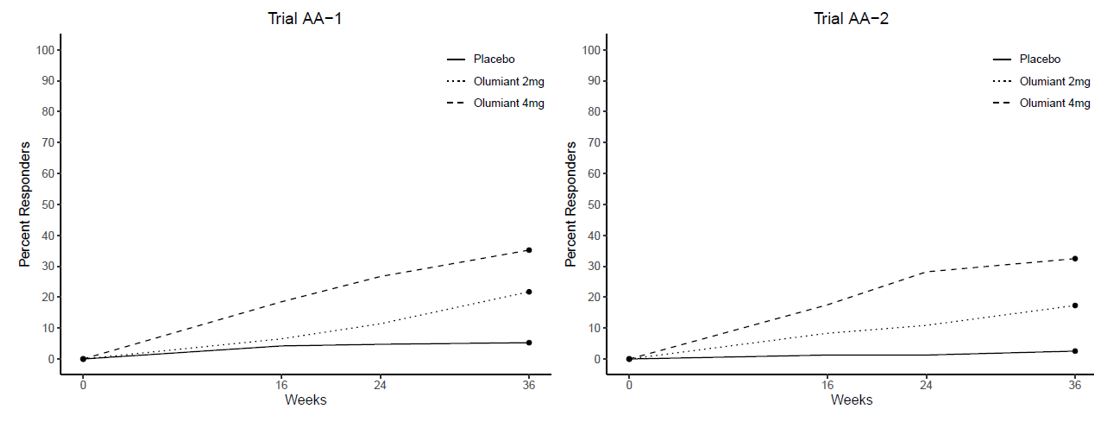 DRUG LABEL: Olumiant
NDC: 0002-4182 | Form: TABLET, FILM COATED
Manufacturer: Eli Lilly and Company
Category: prescription | Type: HUMAN PRESCRIPTION DRUG LABEL
Date: 20260113

ACTIVE INGREDIENTS: baricitinib 2 mg/1 1
INACTIVE INGREDIENTS: Mannitol; Microcrystalline Cellulose; Croscarmellose Sodium; Magnesium Stearate; Polyvinyl Alcohol, Unspecified; Titanium Dioxide; Polyethylene Glycol, Unspecified; Talc; Soybean Lecithin; Ferric Oxide Red

HIGHLIGHTS OF PRESCRIBING INFORMATION

These highlights do not include all the information needed to use OLUMIANT safely and effectively. See full prescribing information for OLUMIANT.
OLUMIANT (baricitinib) tablets, for oral use
Initial U.S. Approval: 2018

RECENT MAJOR CHANGES

Boxed Warning | 05/2022
Indications and Usage, COVID-19 (1.2) | 05/2022
Indications and Usage, Alopecia Areata (1.3) | 06/2022
Dosage and Administration (2.1, 2.2, 2.3, 2.8) | 05/2022
Dosage and Administration (2.4, 2.5, 2.6, 2.7) | 06/2022
Warnings and Precautions (5.1, 5.2, 5.3, 5.4, 5.5) | 12/2021
Warnings and Precautions (5.8) | 05/2022

WARNING: SERIOUS INFECTIONS, MORTALITY, MALIGNANCY, MAJOR ADVERSE CARDIOVASCULAR EVENTS (MACE), and THROMBOSIS

See full prescribing information for complete boxed warning.

- Increased risk of serious bacterial, fungal, viral and opportunistic infections leading to hospitalization or death, including tuberculosis (TB). Interrupt treatment with OLUMIANT if serious infection occurs until the infection is controlled. OLUMIANT should not be given to patients with active tuberculosis. Test for latent TB before and during therapy, except for COVID-19; treat latent TB prior to use. Monitor all patients for active TB during treatment, even patients with initial negative, latent TB test. (5.1)
- Higher rate of all-cause mortality, including sudden cardiovascular death with another Janus kinase inhibitor (JAK) vs. TNF blockers in rheumatoid arthritis (RA) patients. (5.2)
- Malignancies have occurred in patients treated with OLUMIANT. Higher rate of lymphomas and lung cancers with another JAK inhibitor vs. TNF blockers in RA patients. (5.3)
- Higher rate of MACE (defined as cardiovascular death, myocardial infarction, and stroke) with another JAK inhibitor vs. TNF blockers in RA patients. (5.4)
- Thrombosis has occurred in patients treated with OLUMIANT. Increased incidence of pulmonary embolism, venous and arterial thrombosis with another JAK inhibitor vs. TNF blockers. (5.5)

1 INDICATIONS AND USAGE

OLUMIANT® is a Janus kinase (JAK) inhibitor indicated for:

- the treatment of adult patients with moderately to severely active rheumatoid arthritis who have had an inadequate response to one or more TNF blockers. (1.1)

Limitations of Use: Not recommended for use in combination with other JAK inhibitors, biologic DMARDs, or with potent immunosuppressants such as azathioprine and cyclosporine. (1.1)

- the treatment of COVID-19 in hospitalized adults requiring supplemental oxygen, non-invasive or invasive mechanical ventilation, or ECMO. (1.2)
- the treatment of adult patients with severe alopecia areata. (1.3)

Limitations of Use: Not recommended for use in combination with other JAK inhibitors, biologic immunomodulators, cyclosporine or other potent immunosuppressants. (1.3)

2 DOSAGE AND ADMINISTRATION

Administration Instructions:

- See the full prescribing information for recommended evaluations and immunizations prior to treatment. (2.1)
- Rheumatoid Arthritis and Alopecia Areata: Avoid initiation or interrupt OLUMIANT in patients with anemia (hemoglobin <8 g/dL), lymphopenia (ALC <500 cells/mm^3) or neutropenia (ANC <1000 cells/mm^3). (2.1, 2.5, 5.8)
- COVID-19: Avoid initiation or interrupt OLUMIANT in patients with lymphopenia (ALC <200 cells/mm^3) or neutropenia (ANC <500 cells/mm^3). (2.1, 2.5, 5.8)

Recommended Dosage:

Rheumatoid Arthritis:

- 2 mg once daily. (2.2)
- OLUMIANT may be used as monotherapy or in combination with methotrexate or other non-biologic DMARDs. (2.2)

COVID-19:

- 4 mg once daily for up to 14 days. (2.3)

Alopecia Areata:

- 2 mg once daily. Increase to 4 mg once daily, if the response to treatment is not adequate. (2.4)
- For patients with nearly complete or complete scalp hair loss, with or without substantial eyelash or eyebrow hair loss, consider treating with 4 mg once daily. (2.4)
- Reduce the dose to 2 mg once daily when an adequate response has been achieved. (2.4)

Dosage Modifications in Patients with Renal or Hepatic Impairment, or Cytopenias

- See the full prescribing information for dosage modifications by indication. (2.5, 2.6, 5.8)

3 DOSAGE FORMS AND STRENGTHS

Tablets: 4 mg, 2 mg, 1 mg (3)

4 CONTRAINDICATIONS

None.

5 WARNINGS AND PRECAUTIONS

- Hypersensitivity: Serious reactions have been reported. Discontinue OLUMIANT if a serious hypersensitivity reaction occurs. (5.6)
- Gastrointestinal Perforations: Monitor patients who may be at increased risk and evaluate promptly new onset of abdominal symptoms. (5.7)
- Laboratory Abnormalities: Monitor for changes in lymphocytes, neutrophils, hemoglobin, liver enzymes, and lipids. (5.8)
- Vaccinations: Avoid use with live vaccines. (5.9)

6 ADVERSE REACTIONS

Adverse reactions reported in clinical trials (≥1%) are:

- Rheumatoid Arthritis: upper respiratory tract infections (URTIs), nausea, herpes simplex, and herpes zoster. (6.1)
- COVID-19: increases of liver enzymes, thrombocytosis, creatine phosphokinase increases, neutropenia, deep vein thrombosis, pulmonary embolism, and urinary tract infection (UTI) (6.1)
- Alopecia Areata: URTIs, headache, acne, hyperlipidemia, creatine phosphokinase increase, UTI, liver enzyme elevations, folliculitis, fatigue, lower respiratory tract infections, nausea, genital Candida infections, anemia, neutropenia, abdominal pain, herpes zoster, and weight increase (6.1)

To report SUSPECTED ADVERSE REACTIONS, contact Eli Lilly and Company at 1-800-LillyRx (1-800-545-5979) or FDA at 1-800-FDA-1088 or www.fda.gov/medwatch.

7 DRUG INTERACTIONS

In patients taking strong Organic Anion Transporter 3 (OAT3) inhibitors (e.g., probenecid) the recommended dosage should be reduced. (2.7, 7.1)

8 USE IN SPECIFIC POPULATIONS

- Hepatic Impairment: Not recommended in patients with RA or AA and severe hepatic impairment. OLUMIANT has not been studied in patients with COVID-19 and severe hepatic impairment. (2.5, 8.6)
- Renal Impairment: Not recommended in COVID-19 patients with eGFR <15 mL/min/1.73m^2, who are on dialysis, have ESRD, or acute kidney injury. OLUMIANT is not recommend in patients with RA or AA with eGFR <30 mL/min/1.73m^2. (2.6, 8.7)
- Pregnancy: Based on animal data, may cause fetal harm. (8.1, 8.3)
- Lactation: Advise not to breastfeed. (8.2)

FULL PRESCRIBING INFORMATION

WARNING: SERIOUS INFECTIONS, MORTALITY, MALIGNANCY, MAJOR ADVERSE CARDIOVASCULAR EVENTS (MACE), and THROMBOSIS

SERIOUS INFECTIONS

Patients treated with OLUMIANT are at risk for developing serious infections that may lead to hospitalization or death [see Warnings and Precautions (5.1) and Adverse Reactions (6.1)]. Most patients with rheumatoid arthritis who developed these infections were taking concomitant immunosuppressants such as methotrexate or corticosteroids.

If a serious infection develops, interrupt OLUMIANT until the infection is controlled.

Reported infections include:

- Active tuberculosis, which may present with pulmonary or extrapulmonary disease. OLUMIANT should not be given to patients with active tuberculosis. Patients, except those with COVID-19, should be tested for latent tuberculosis before initiating OLUMIANT and during therapy. If positive, start treatment for latent infection prior to OLUMIANT use.
- Invasive fungal infections, including candidiasis and pneumocystosis. Patients with invasive fungal infections may present with disseminated, rather than localized, disease.
- Bacterial, viral, and other infections due to opportunistic pathogens.

The risks and benefits of treatment with OLUMIANT should be carefully considered prior to initiating therapy in patients with chronic or recurrent infection.

Patients should be closely monitored for the development of signs and symptoms of infection during and after treatment with OLUMIANT including the possible development of tuberculosis in patients who tested negative for latent tuberculosis infection prior to initiating therapy [see Warnings and Precautions (5.1)].

MORTALITY

In a large, randomized, postmarketing safety study in rheumatoid arthritis (RA) patients 50 years of age and older with at least one cardiovascular risk factor comparing another Janus kinase (JAK) inhibitor to tumor necrosis factor (TNF) blockers, a higher rate of all-cause mortality, including sudden cardiovascular death, was observed with the JAK inhibitor [see Warnings and Precautions (5.2)].

MALIGNANCIES

Lymphoma and other malignancies have been observed in patients treated with OLUMIANT. In RA patients treated with another JAK inhibitor, a higher rate of malignancies (excluding non-melanoma skin cancer (NMSC)) was observed when compared with TNF blockers. Patients who are current or past smokers are at additional increased risk [see Warnings and Precautions (5.3)].

MAJOR ADVERSE CARDIOVASCULAR EVENTS

In RA patients 50 years of age and older with at least one cardiovascular risk factor treated with another JAK inhibitor, a higher rate of major adverse cardiovascular events (MACE) (defined as cardiovascular death, myocardial infarction, and stroke) was observed when compared with TNF blockers. Patients who are current or past smokers are at additional increased risk. Discontinue OLUMIANT in patients that have experienced a myocardial infarction or stroke [see Warnings and Precautions (5.4)].

THROMBOSIS

Thrombosis, including deep venous thrombosis and pulmonary embolism, has been observed at an increased incidence in patients treated with OLUMIANT compared to placebo. In addition, there were cases of arterial thrombosis. Many of these adverse events were serious and some resulted in death. In RA patients 50 years of age and older with at least one cardiovascular risk factor treated with another JAK inhibitor, a higher rate of thrombosis was observed when compared with TNF blockers. Avoid OLUMIANT in patients at risk. Patients with symptoms of thrombosis should discontinue OLUMIANT and be promptly evaluated. [see Warnings and Precautions (5.5)].

1 INDICATIONS AND USAGE

1.1 Rheumatoid Arthritis

OLUMIANT® (baricitinib) is indicated for the treatment of adult patients with moderately to severely active rheumatoid arthritis who have had an inadequate response to one or more tumor necrosis factor (TNF) blockers.

Limitations of Use: Not recommended for use in combination with other JAK inhibitors, biologic disease-modifying antirheumatic drugs (DMARDs), or with potent immunosuppressants such as azathioprine and cyclosporine.

1.2 Coronavirus Disease 2019 (COVID-19)

OLUMIANT is indicated for the treatment of coronavirus disease 2019 (COVID-19) in hospitalized adults requiring supplemental oxygen, non-invasive or invasive mechanical ventilation, or extracorporeal membrane oxygenation (ECMO).

1.3 Alopecia Areata

OLUMIANT is indicated for the treatment of adult patients with severe alopecia areata.

Limitations of Use: Not recommended for use in combination with other JAK inhibitors, biologic immunomodulators, cyclosporine or other potent immunosuppressants.

2 DOSAGE AND ADMINISTRATION

2.1 Recommended Evaluations and Immunization Prior to Treatment Initiation

Prior to OLUMIANT treatment initiation, consider performing the following evaluations:

- Active and latent tuberculosis (TB) infection evaluation – OLUMIANT should not be given to patients with active tuberculosis (TB). If latent infection is positive in patients with rheumatoid arthritis or alopecia areata, consider treatment for TB prior to OLUMIANT use [see Warnings and Precautions (5.1)].
- Viral hepatitis screening in accordance with clinical guidelines [see Warnings and Precautions (5.1)].
- Complete blood count – Assess baseline values and verify whether treatment can be initiated:
  - In patients with rheumatoid arthritis or alopecia areata, OLUMIANT initiation is not recommended in patients with an absolute lymphocyte count (ALC) <500 cells/μl, absolute neutrophil count (ANC) <1000 cells/μl, or hemoglobin level <8 g/dL.
  - In patients with COVID-19, OLUMIANT initiation is not recommended if the ALC is <200 cells/μl or if the ANC is <500 cells/μl.
  Monitor complete blood counts during treatment and modify dosage as recommended [see Dosage and Administration (2.5) and Warnings and Precautions (5.7)].
- Baseline hepatic and renal function – Assess baseline values and monitor patients for laboratory changes. Modify dosage based on hepatic and renal impairment, and laboratory abnormalities [see Dosage and Administration (2.5) and Warnings and Precautions (5.7)].

In patients with rheumatoid arthritis or alopecia areata, update immunizations in agreement with current immunization guidelines [see Warnings and Precautions (5.9)].

2.2 Dosage Recommendations in Rheumatoid Arthritis

The recommended dosage of OLUMIANT is 2 mg once daily orally, with or without food [see Clinical Pharmacology (12.3)]. An alternative administration for patients unable to swallow tablets may be used [see Dosage and Administration (2.8)]. OLUMIANT may be used as monotherapy or in combination with methotrexate or other non-biologic DMARDs.

2.3 Dosage Recommendations in COVID-19

The recommended dosage of OLUMIANT for adults is 4 mg once daily orally, with or without food, for 14 days or until hospital discharge, whichever occurs first. An alternative administration for patients unable to swallow tablets may be used [see Dosage and Administration (2.8)].

2.4 Dosage Recommendations in Alopecia Areata

The recommended dosage of OLUMIANT is 2 mg once daily orally, with or without food. Increase to 4 mg once daily if the response to treatment is not adequate.

For patients with nearly complete or complete scalp hair loss, with or without substantial eyelash or eyebrow hair loss, consider treating with 4 mg once daily, with or without food.

Once patients achieve an adequate response to treatment with 4 mg, decrease the dosage to 2 mg once daily.

2.5 Dosage Modifications Due to Infections, Cytopenias and Anemia

Rheumatoid Arthritis and Alopecia Areata

- Avoid use of OLUMIANT in patients with active, serious or opportunistic infection, including localized infections. If a patient develops a serious infection hold treatment with OLUMIANT until the infection is controlled [see Warnings and Precautions (5.1)].
- Dosage modifications for patients with rheumatoid arthritis or alopecia areata and cytopenias or anemia are described in Table 1.

Table 1: Dosage Modifications for Cytopenias and Anemia in Patients with Rheumatoid Arthritis or Alopecia Areata
Laboratory Analyte | Laboratory Analyte Value | Recommendation
Absolute Lymphocyte Count (ALC) | ≥500 cells/μL | Maintain dosage
Absolute Lymphocyte Count (ALC) | <500 cells/μL | Interrupt OLUMIANT until ALC ≥500 cells/μL
Absolute Neutrophil Count (ANC) | ≥1000 cells/μL | Maintain dosage
Absolute Neutrophil Count (ANC) | <1000 cells/μL | Interrupt OLUMIANT until ANC ≥1000 cells/μL
Hemoglobin | ≥8 g/dL | Maintain dosage
Hemoglobin | <8 g/dL | Interrupt OLUMIANT until hemoglobin ≥8 g/dL

COVID-19

- Monitor patients for signs and symptoms of new infections during treatment with OLUMIANT. The risks and benefits of treatment with OLUMIANT in COVID-19 patients with other concurrent infections should be considered [see Warnings and Precautions (5.1)].
- Dosage modifications for patients with COVID-19 and cytopenias are described in Table 2.

Table 2: Dosage Modifications for Cytopenias in Patients with COVID-19
Laboratory Analyte | Laboratory Analyte Value | Recommendation
Absolute Lymphocyte Count (ALC) | ≥200 cells/μL | Maintain dosage
Absolute Lymphocyte Count (ALC) | <200 cells/μL | Interrupt OLUMIANT until ALC ≥200 cells/μL
Absolute Neutrophil Count (ANC) | ≥500 cells/μL | Maintain dosage
Absolute Neutrophil Count (ANC) | <500 cells/μL | Interrupt OLUMIANT until ANC ≥500 cells/μL

2.6 Dosage Modifications for Patients with Renal Impairment or Hepatic Impairment

Rheumatoid Arthritis

Renal Impairment

Dosage modifications for patients with rheumatoid arthritis and renal impairment are described in Table 3.

Table 3: Dosage Modifications for Patients with Rheumatoid Arthritis and Renal Impairment
Renal Impairment Stage | Estimated Glomerular Filtration Rate (eGFR) | Recommendation
Mild | 60 – <90 mL/minute/1.73 m^2 | 2 mg once daily
Moderate | 30 - <60 mL/min/1.73 m^2 | 1 mg once daily
Severe | <30 mL/minute/1.73 m^2 | Not recommended

Hepatic Impairment

- OLUMIANT is not recommended for use in patients with severe hepatic impairment.
- Interrupt OLUMIANT, if increases in ALT or AST are observed and drug-induced liver injury (DILI) is suspected, until the diagnosis of DILI is excluded [see Warnings and Precautions (5.8)].

COVID-19

Renal Impairment

- Dosage modifications for patients with COVID-19 and renal impairment are described in Table 4.

Table 4: Dosage Modifications for Patients with COVID-19 and Renal Impairment
Renal Impairment Stage | Estimated Glomerular Filtration Rate (eGFR) | Recommendation
Mild | 60 - <90 mL/min/1.73m^2 | 4 mg once daily
Moderate | 30 - <60 mL/min/1.73m^2 | 2 mg once daily
Severe | 15 - <30 mL/min/1.73m^2 | 1 mg once daily
End Stage Renal Disease, Patients on Dialysis, or Acute Kidney Injury | <15 mL/min/1.73m^2 | Not recommended

Hepatic Impairment

- It is not known if dosage adjustment is needed in patients with COVID-19 and severe hepatic impairment. OLUMIANT should only be used in patients with COVID-19 and severe hepatic impairment if the potential benefit outweighs the potential risk.
- Interrupt OLUMIANT, if increases in ALT or AST are observed and DILI is suspected, until the diagnosis of DILI is excluded [see Warnings and Precautions (5.8)].

Alopecia Areata

Renal Impairment

Dosage modifications for patients with alopecia areata and renal impairment are described in Table 5.

Table 5: Dosage Modifications for Patients with Alopecia Areata and Renal Impairment
Renal Impairment Stage | Estimated Glomerular Filtration Rate (eGFR) | Recommendation
Renal Impairment Stage | Estimated Glomerular Filtration Rate (eGFR) | If the recommended dosage is 2 mg once daily | If the recommended dosage is 4 mg once daily
Mild | 60 – <90 mL/minute/1.73 m^2 | Maintain dosage
Moderate | 30 – <60 mL/min/1.73 m^2 | Reduce to 1 mg once daily | Reduce to 2 mg once daily
Severe | <30 mL/minute/1.73 m^2 | Not recommended

Hepatic Impairment

- OLUMIANT is not recommended for use in patients with severe hepatic impairment.
- Interrupt OLUMIANT, if increases in ALT or AST are observed and DILI is suspected, until the diagnosis of DILI is excluded [see Warnings and Precautions (5.8)].

2.7 Dosage Modifications Due to Drug Interactions

Rheumatoid Arthritis, COVID-19 or Alopecia Areata

The recommended dosage of OLUMIANT in patients taking strong Organic Anion Transporter 3 (OAT3) inhibitors, such as probenecid, are shown in Table 6 [see Drug Interactions (7.1) and Clinical Pharmacology (12.3)].

Table 6: Dosage Modifications when Coadministered with Strong OAT3 Inhibitors in Patients With Rheumatoid Arthritis, COVID-19 or Alopecia Areata
Concomitant Medication | Recommendation
Strong OAT3 inhibitors (e.g., probenecid) | If the recommended dosage is 4 mg once daily, reduce dosage to 2 mg once daily.
Strong OAT3 inhibitors (e.g., probenecid) | If the recommended dosage is 2 mg once daily, reduce dosage to 1 mg once daily.
Strong OAT3 inhibitors (e.g., probenecid) | If the recommended dosage is 1 mg once daily, consider discontinuing probenecid.

2.8 Alternative Administration for Patients Unable to Swallow Tablets

For patients who are unable to swallow whole tablets, an alternative mode of administration may be considered:

- Oral dispersion
- Gastrostomy tube (G tube)
- Nasogastric tube (NG tube) or orogastric tube (OG tube)

Intact tablets are not hazardous. Tablets may be crushed to facilitate dispersion. It is not known if powder from the crushed tablets may constitute a reproductive hazard to the preparer. If tablets are crushed, use proper control measures (e.g., ventilated enclosure) or personal protective equipment (i.e., N95 respirator). Dispersed tablets are stable in water for up to 4 hours.

Preparation Instructions for Alternative Administration:

- Oral administration of dispersed tablets in water: For patients who are unable to swallow whole tablets, 1-mg, 2-mg, or 4-mg baricitinib tablet(s), or any combination of tablets necessary to achieve the desired dose up to 4-mg may be placed in a container with approximately 10 mL (5 mL minimum) of room temperature water, dispersed by gently swirling the tablet(s) and immediately taken orally. The container should be rinsed with an additional 10 mL (5 mL minimum) of room temperature water and the entire contents swallowed by the patient (Table 7).
- Administration via G tube: For patients with a G tube, 1-mg, 2-mg, or 4-mg baricitinib tablet(s), or any combination of tablets necessary to achieve the desired dose up to 4-mg may be placed in a container with approximately 15 mL (10 mL minimum) of room temperature water and dispersed with gentle swirling. Ensure the tablet(s) are sufficiently dispersed to allow free passage through the tip of the syringe. Withdraw entire contents from the container into an appropriate syringe and immediately administer through the gastric feeding tube. Rinse container with approximately 15 mL (10 mL minimum) of room temperature water, withdraw the contents into the syringe, and administer through the tube (Table 7).
- Administration via NG or OG tube: For patients with a NG or OG tube, 1-mg, 2-mg, or 4-mg baricitinib tablet(s), or a combination of tablets necessary to achieve the desired dose up to 4-mg may be placed into a container with approximately 30 mL of room temperature water and dispersed with gentle swirling. Ensure the tablet(s) are sufficiently dispersed to allow free passage through the tip of the syringe. Withdraw the entire contents from the container into an appropriate syringe and immediately administer through the enteral feeding tube. To avoid clogging of small diameter tubes (smaller than 12 Fr), the syringe can be held horizontally and shaken during administration. Rinse container with a sufficient amount (minimum of 15 mL) of room temperature water, withdraw the contents into the syringe, and administer through the tube (Table 7).

Table 7: Dispersion and Rinse Volume for Alternative Administration
Administration via | Dispersion Volume | Container Rinse Volume
Oral dispersion | 10 mL | 10 mL
G tube | 15 mL | 15 mL
NG tube or OG tube | 30 mL | 15 mL

3 DOSAGE FORMS AND STRENGTHS

OLUMIANT is available as debossed, film-coated tablets:

- 1 mg tablet contains a recessed area on each face of the tablet surface, is very light pink, round, debossed with “Lilly” on one side and “1” on the other.
- 2 mg tablet contains a recessed area on each face of the tablet surface, is light pink, oblong, debossed with “Lilly” on one side and “2” on the other.
- 4 mg tablet contains a recessed area on each face of the tablet surface, is medium pink, round, debossed with “Lilly” on one side and “4” on the other.

4 CONTRAINDICATIONS

None.

5 WARNINGS AND PRECAUTIONS

5.1 Serious Infections

Serious and sometimes fatal infections due to bacterial, mycobacterial, invasive fungal, viral, or other opportunistic pathogens have been reported in patients with rheumatoid arthritis receiving OLUMIANT. The most common serious infections reported with OLUMIANT included pneumonia, herpes zoster, and urinary tract infection [see Adverse Reactions (6.1)]. Among opportunistic infections, tuberculosis, multidermatomal herpes zoster, esophageal candidiasis, pneumocystosis, acute histoplasmosis, cryptococcosis, cytomegalovirus, and BK virus were reported with OLUMIANT. Some patients have presented with disseminated rather than localized disease, and were often taking concomitant immunosuppressants such as methotrexate or corticosteroids.

Avoid use of OLUMIANT in patients with an active, serious infection, including localized infections. Consider the risks and benefits of treatment prior to initiating OLUMIANT in patients:

- with chronic or recurrent infection
- who have been exposed to tuberculosis
- with a history of a serious or an opportunistic infection
- who have resided or traveled in areas of endemic tuberculosis or endemic mycoses; or
- with underlying conditions that may predispose them to infection.

In patients with rheumatoid arthritis or alopecia areata, closely monitor for the development of signs and symptoms of infection during and after treatment with OLUMIANT. Interrupt OLUMIANT in patients with rheumatoid arthritis or alopecia areata, if the patient develops a serious infection, an opportunistic infection, or sepsis. A patient who develops a new infection during treatment with OLUMIANT should undergo prompt and complete diagnostic testing appropriate for an immunocompromised patient; appropriate antimicrobial therapy should be initiated, the patient should be closely monitored, and OLUMIANT should be interrupted if the patient is not responding to therapy. Do not resume OLUMIANT until the infection is controlled.

In patients with COVID-19, monitor for signs and symptoms of new infections during and after treatment with OLUMIANT. There is limited information regarding the use of OLUMIANT in patients with COVID-19 and concomitant active serious infections. The risks and benefits of treatment with OLUMIANT in COVID-19 patients with other concurrent infections should be considered.

Tuberculosis

Evaluate patients for active infection prior to administration of OLUMIANT. OLUMIANT should not be given to patients with active TB.

Test patients with rheumatoid arthritis or alopecia areata for latent tuberculosis. Patients with rheumatoid arthritis or alopecia areata and latent tuberculosis (TB) should be treated with standard antimycobacterial therapy before initiating OLUMIANT. Consider anti-TB therapy prior to initiation of OLUMIANT in patients with a history of latent or active TB in whom an adequate course of treatment cannot be confirmed, and for patients with a negative test for latent TB but who have risk factors for TB infection. Consultation with a physician with expertise in the treatment of TB is recommended to aid in the decision about whether initiating anti-TB therapy is appropriate for an individual patient.

During OLUMIANT use, monitor patients for the development of signs and symptoms of TB, including patients who tested negative for latent TB infection prior to initiating therapy.

Viral Reactivation

Viral reactivation, including cases of herpes virus reactivation (e.g., herpes zoster), were reported in clinical studies with OLUMIANT. If a patient develops herpes zoster, interrupt OLUMIANT treatment until the episode resolves.

The impact of OLUMIANT on chronic viral hepatitis reactivation is unknown. Patients with evidence of active hepatitis B or C infection were excluded from clinical trials. In clinical trials in patients with rheumatoid arthritis or alopecia areata, patients who were positive for hepatitis C antibody but negative for hepatitis C virus RNA were permitted to enroll. Patients with positive hepatitis B surface antibody and hepatitis B core antibody, without hepatitis B surface antigen, were permitted to enroll; such patients should be monitored for expression of hepatitis B virus (HBV) DNA. Should HBV DNA be detected, consult with a hepatologist. Perform screening for viral hepatitis in accordance with clinical guidelines before starting therapy with OLUMIANT.

5.2 Mortality

In a large, randomized, postmarketing safety study of another JAK inhibitor in RA patients 50 years of age and older with at least one cardiovascular risk factor, a higher rate of all-cause mortality, including sudden cardiovascular death, was observed in patients treated with the JAK inhibitor compared with TNF blockers. Consider the benefits and risks for the individual patient prior to initiating or continuing therapy with OLUMIANT.

5.3 Malignancy and Lymphoproliferative Disorders

Malignancies were observed in clinical studies of OLUMIANT [see Adverse Reactions (6.1)].

In a large, randomized, postmarketing safety study of another JAK inhibitor in RA patients, a higher rate of malignancies (excluding non-melanoma skin cancer (NMSC)) was observed in patients treated with the JAK inhibitor compared to those treated with TNF blockers. A higher rate of lymphomas was observed in patients treated with the JAK inhibitor compared to those treated with TNF blockers. A higher rate of lung cancers was observed in current or past smokers treated with the JAK inhibitor compared to those treated with TNF blockers. In this study, current or past smokers had an additional increased risk of overall malignancies.

Consider the benefits and risks for the individual patient prior to initiating or continuing therapy with OLUMIANT, particularly in patients with a known malignancy (other than successfully treated NMSC), patients who develop a malignancy, and patients who are current or past smokers.

Non-melanoma skin cancers

Non-melanoma skin cancers (NMSCs) have been reported in patients treated with OLUMIANT. Periodic skin examination is recommended for patients who are at increased risk for skin cancer.

5.4 Major Adverse Cardiovascular Events

In a large, randomized, postmarketing safety study of another JAK inhibitor in RA patients 50 years of age and older with at least one cardiovascular risk factor, a higher rate of major adverse cardiovascular events (MACE) defined as cardiovascular death, non-fatal myocardial infarction (MI), and non-fatal stroke was observed with the JAK inhibitor compared to those treated with TNF blockers. Patients who are current or past smokers are at additional increased risk.

Consider the benefits and risks for the individual patient prior to initiating or continuing therapy with OLUMIANT, particularly in patients who are current or past smokers and patients with other cardiovascular risk factors. Patients should be informed about the symptoms of serious cardiovascular events and the steps to take if they occur. Discontinue OLUMIANT in patients that have experienced a myocardial infarction or stroke.

5.5 Thrombosis

Thrombosis, including deep venous thrombosis (DVT) and pulmonary embolism (PE), has been observed at an increased incidence in patients treated with OLUMIANT compared to placebo. In addition, arterial thrombosis events in the extremities have been reported in clinical studies with OLUMIANT. Many of these adverse events were serious and some resulted in death. There was no clear relationship between platelet count elevations and thrombotic events. In a large, randomized, postmarketing safety study of another JAK inhibitor in RA patients 50 years of age and older with at least one cardiovascular risk factor, higher rates of overall thrombosis, DVT, and PE were observed compared to those treated with TNF blockers.

If clinical features of DVT/PE or arterial thrombosis occur, patients should discontinue OLUMIANT and be evaluated promptly and treated appropriately. Avoid OLUMIANT in patients that may be at increased risk of thrombosis.

5.6 Hypersensitivity

Reactions such as angioedema, urticaria, and rash that may reflect drug hypersensitivity have been observed in patients receiving OLUMIANT, including serious reactions. If a serious hypersensitivity reaction occurs, promptly discontinue OLUMIANT while evaluating the potential causes of the reaction [see Adverse Reactions (6.2)].

5.7 Gastrointestinal Perforations

Gastrointestinal perforations have been reported in clinical studies with OLUMIANT.

Monitor OLUMIANT-treated patients who may be at increased risk for gastrointestinal perforation (e.g., patients with a history of diverticulitis). Evaluate promptly patients presenting with new onset abdominal symptoms for early identification of gastrointestinal perforation.

5.8 Laboratory Abnormalities

Neutropenia – Treatment with OLUMIANT was associated with an increased incidence of neutropenia (ANC less than 1000 cells/mm^3) compared to placebo.

In patients with rheumatoid arthritis or alopecia areata, avoid initiation or interrupt OLUMIANT treatment in patients with an ANC less than 1000 cells/mm^3.

In patients with COVID-19, there is limited information regarding use of OLUMIANT in patients with ANC less than 1000 cells/mm^3. Avoid initiation or interrupt OLUMIANT treatment in patients with COVID-19 and an ANC less than 500 cells/mm^3.

Evaluate at baseline and thereafter according to routine patient management. Adjust dosing based on ANC [see Dosage and Administration (2.1, 2.5) and Adverse Reactions (6.1)].

Lymphopenia – ALC less than 500 cells/mm^3 were reported in OLUMIANT clinical trials. Lymphocyte counts less than the lower limit of normal were associated with infection in patients treated with OLUMIANT, but not placebo.

In patients with rheumatoid arthritis or alopecia areata, avoid initiation or interrupt OLUMIANT treatment in patients with an ALC less than 500 cells/mm^3.

In patients with COVID-19, there is limited information regarding use of OLUMIANT in patients with ALC less than 200 cells/mm^3. Avoid initiation or interrupt OLUMIANT treatment in patients with COVID-19 and an ALC less than 200 cells/mm^3.

Evaluate at baseline and thereafter according to routine patient management. Adjust dosing based on ALC [see Dosage and Administration (2.1, 2.5)].

Anemia – Decreases in hemoglobin levels to less than 8 g/dL were reported in OLUMIANT clinical trials. In patients with rheumatoid arthritis or alopecia areata, avoid initiation or interrupt OLUMIANT treatment in patients with hemoglobin less than 8 g/dL. Evaluate at baseline and thereafter according to routine patient management. Adjust dosing based on hemoglobin levels [see Dosage and Administration (2.1, 2.5)].

In patients with COVID-19, there is limited information regarding use of OLUMIANT in patients with hemoglobin less than 8 g/dL.

Liver Enzyme Elevations – Treatment with OLUMIANT was associated with increased incidence of liver enzyme elevation compared to placebo. Increases of ALT ≥5 times the upper limit of normal (ULN) and increases of AST ≥10 times the ULN were observed in patients in OLUMIANT clinical trials. Evaluate at baseline and thereafter according to routine patient management. Prompt investigation of the cause of liver enzyme elevation is recommended to identify potential cases of drug-induced liver injury. If increases in ALT or AST are observed and drug-induced liver injury is suspected, interrupt OLUMIANT until this diagnosis is excluded [see Adverse Reactions (6.1)].

Lipid Elevations – Treatment with OLUMIANT was associated with increases in lipid parameters, including total cholesterol, low-density lipoprotein (LDL) cholesterol, and high-density lipoprotein (HDL) cholesterol. Assessment of lipid parameters should be performed approximately 12 weeks following OLUMIANT initiation in patients with rheumatoid arthritis or alopecia areata [see Adverse Reactions (6.1)]. Manage patients according to clinical guidelines for the management of hyperlipidemia.

5.9 Vaccinations

Avoid use of live vaccines with OLUMIANT. Update immunizations in patients with rheumatoid arthritis or alopecia areata prior to initiating OLUMIANT therapy in agreement with current immunization guidelines.

6 ADVERSE REACTIONS

The following clinically significant adverse reactions are described elsewhere in the labeling:

- Serious Infections [see Warnings and Precautions (5.1)]
- Mortality [see Warnings and Precautions (5.2)]
- Malignancy and Lymphoproliferative Disorders [see Warnings and Precautions (5.3)]
- Major Adverse Cardiovascular Events [see Warnings and Precautions (5.4)]
- Thrombosis [see Warnings and Precautions (5.5)]
- Hypersensitivity [see Warnings and Precautions (5.6)]
- Gastrointestinal Perforations [see Warnings and Precautions (5.7)]
- Laboratory Abnormalities [see Warnings and Precautions (5.8)]

6.1 Clinical Trials Experience

Because clinical studies are conducted under widely varying conditions, adverse reaction rates observed in the clinical studies of a drug cannot be directly compared to rates in the clinical studies of another drug and may not predict the rates observed in a broader patient population in clinical practice.

Adverse Reactions in Patients with Rheumatoid Arthritis

The safety of OLUMIANT was evaluated in six randomized double-blind placebo-controlled studies (three Phase 2, three Phase 3) and a long-term extension study in patients with moderately to severely active RA. Patients were randomized to placebo (1070 patients), OLUMIANT 2 mg (479 patients), or baricitinib 4 mg (997 patients).

Patients could be switched to baricitinib 4 mg from placebo or OLUMIANT 2 mg from as early as Week 12 depending on the study design. All patients initially randomized to placebo were switched to baricitinib 4 mg by Week 24.

During the 16-week treatment period, adverse events leading to discontinuation of treatment were reported by 35 patients (11.4 per 100 patient-years) treated with placebo, 17 patients (12.1 per 100 patient-years) with OLUMIANT 2 mg, and 40 patients (13.4 per 100 patient-years) treated with baricitinib 4 mg.

During 0 to 52-week exposure, adverse events leading to discontinuation of treatment were reported by 31 patients (9.2 per 100 patient-years) with OLUMIANT 2 mg, and 92 patients (10.2 per 100 patient-years) treated with baricitinib 4 mg.

Overall Infections – During the 16-week treatment period, infections were reported by 253 patients (82.1 per 100 patient-years) treated with placebo, 139 patients (99.1 per 100 patient-years) treated with OLUMIANT 2 mg, and 298 patients (100.1 per 100 patient-years) treated with baricitinib 4 mg.

During 0 to 52-week exposure, infections were reported by 200 patients (59.6 per 100 patients-years) treated with OLUMIANT 2 mg, and 500 patients (55.3 per 100 patient-years) treated with baricitinib 4 mg.

In the 0 to 52-week exposure population, the most commonly reported infections with OLUMIANT were viral upper respiratory tract infection, upper respiratory tract infection, urinary tract infection, and bronchitis.

Serious Infections – During the 16-week treatment period, serious infections were reported in 13 patients (4.2 per 100 patient-years) treated with placebo, 5 patients (3.6 per 100 patient-years) treated with OLUMIANT 2 mg, and 11 patients (3.7 per 100 patient-years) treated with baricitinib 4 mg.

During 0 to 52-week exposure, serious infections were reported in 14 patients (4.2 per 100 patient-years) treated with OLUMIANT 2 mg and 32 patients (3.5 per 100 patient-years) treated with baricitinib 4 mg.

In the 0 to 52-week exposure population, the most commonly reported serious infections with OLUMIANT were pneumonia, herpes zoster, and urinary tract infection [see Warnings and Precautions (5.1)].

Tuberculosis – During the 16-week treatment period, no events of tuberculosis were reported.

During 0 to 52-week exposure, events of tuberculosis were reported in 0 patients treated with OLUMIANT 2 mg and 1 patient (0.1 per 100 patient-years) treated with baricitinib 4 mg [see Warnings and Precautions (5.1)].

Cases of disseminated tuberculosis were also reported.

Opportunistic Infections (excluding tuberculosis) – During the 16-week treatment period, opportunistic infections were reported in 2 patients (0.6 per 100 patient-years) treated with placebo, 0 patients treated with OLUMIANT 2 mg and 2 patients (0.7 per 100 patient-years) treated with baricitinib 4 mg. During 0 to 52-week exposure, opportunistic infections were reported in 1 patient (0.3 per 100 patient-years) treated with OLUMIANT 2 mg and 5 patients (0.6 per 100 patient-years) treated with baricitinib 4 mg [see Warnings and Precautions (5.1)].

Malignancies

During the 16-week treatment period, malignancies excluding non-melanoma skin cancers (NMSC) were reported in 0 patients treated with placebo, 1 patient (0.7 per 100 patient-years) treated with OLUMIANT 2 mg, and 1 patient (0.3 per 100 patient-years) treated with baricitinib 4 mg.

During the 0 to 52-week treatment period, malignancies excluding NMSC were reported in 2 patients (0.6 per 100 patient-years) treated with OLUMIANT 2 mg and 6 patients (0.7 per 100 patient-years) treated with baricitinib 4 mg [see Warnings and Precautions (5.3)].

Thrombosis

Venous Thrombosis – During the 16-week treatment period, venous thromboses (deep vein thrombosis or pulmonary embolism) were reported in 0 patients treated with placebo, 0 patients treated with OLUMIANT 2 mg, and 5 patients (1.7 per 100 patient-years) treated with baricitinib 4 mg. During the 0 to 52-week treatment period, venous thromboses were reported in 2 patients (0.6 per 100 patient-years) treated with OLUMIANT 2 mg and 7 patients (0.8 per 100 patient-years) treated with baricitinib 4 mg.

Arterial Thrombosis – During the 16-week treatment period, arterial thromboses were reported in 1 patient treated with placebo (0.3 per 100 patient-years), 2 patients (1.4 per 100 patient-years) treated with OLUMIANT 2 mg, and 2 patients (0.7 per 100 patient-years) treated with baricitinib 4 mg. During the 0 to 52-week treatment period, arterial thromboses were reported in 3 patients (0.9 per 100 patient-years) treated with OLUMIANT 2 mg and 3 patients (0.3 per 100 patient-years) treated with baricitinib 4 mg.

Laboratory Abnormalities

Neutropenia – During the 16-week treatment period, neutrophil counts below 1000 cells/mm^3 occurred in 0% of patients treated with placebo, 0.6% of patients treated with OLUMIANT 2 mg, and 0.3% of patients treated with baricitinib 4 mg. There were no neutrophil counts below 500 cells/mm^3 observed in any treatment group [see Warnings and Precautions (5.1, 5.8)].

Platelet Elevations – During the 16-week treatment period, increases in platelet counts above 600,000 cells/mm^3 occurred in 1.1% of patients treated with placebo, 1.1% of patients treated with OLUMIANT 2 mg, and 2.0% of patients treated with baricitinib 4 mg. Mean platelet count increased by 3000 cells/mm^3 at 16 weeks in patients treated with placebo, by 15,000 cells/mm^3 at 16 weeks in patients treated with OLUMIANT 2 mg and by 23,000 cells/mm^3 in patients treated with baricitinib 4 mg.

Liver Enzyme Elevations – Events of increases in liver enzymes ≥3 times the ULN were observed in patients treated with OLUMIANT [see Warnings and Precautions (5.8)].

- During the 16-week treatment period, ALT elevations ≥3 times the ULN occurred in 1.0% of patients treated with placebo, 1.7% of patients treated with OLUMIANT 2 mg, and 1.4% of patients treated with baricitinib 4 mg.
- During the 16-week treatment period, AST elevations ≥ 3 times the ULN occurred in 0.8% of patients treated with placebo, 1.3% of patients treated with OLUMIANT 2 mg, and 0.8% of patients treated with baricitinib 4 mg.
- In a phase 3 study of DMARD naive patients, during the 24-week treatment period, ALT and AST elevations ≥3 times the ULN occurred in 1.9% and 0% of patients treated with methotrexate monotherapy, 1.9% and 1.3% of patients treated with baricitinib 4 mg monotherapy, and 4.7% and 1.9% of patients treated with baricitinib 4 mg plus methotrexate.

Lipid Elevations – In controlled clinical trials, OLUMIANT treatment was associated with dose-related increases in lipid parameters including total cholesterol, triglycerides, LDL cholesterol, and HDL cholesterol. Elevations were observed at 12 weeks and remained stable thereafter. During the 12-week treatment period, changes in lipid parameters are summarized below:

- Mean LDL cholesterol increased by 8 mg/dL in patients treated with OLUMIANT 2 mg and by 14 mg/dL in patients treated with baricitinib 4 mg.
- Mean HDL cholesterol increased by 7 mg/dL in patients treated with OLUMIANT 2 mg and by 9 mg/dL in patients treated with baricitinib 4 mg.
- The mean LDL/HDL ratio remained stable.
- Mean triglycerides increased by 7 mg/dL in patients treated with OLUMIANT 2 mg and by 15 mg/dL in patients treated with baricitinib 4 mg.

[See Warnings and Precautions (5.8)].

Creatine Phosphokinase (CPK) – OLUMIANT treatment was associated with increases in CPK within one week of starting OLUMIANT and plateauing after 8 to 12 weeks. At 16 weeks, the mean change in CPK for OLUMIANT 2 mg and baricitinib 4 mg was 37 IU/L and 52 IU/L, respectively.

Creatinine – In controlled clinical trials, dose-related increases in serum creatinine were observed with OLUMIANT treatment. At 52 weeks, the mean increase in serum creatinine was less than 0.1 mg/dL with baricitinib 4 mg. The clinical significance of the observed serum creatinine increases is unknown.

Other Adverse Reactions

Other adverse reactions are summarized in Table 8.

Table 8: Adverse Reactions Occurring in Greater Than or Equal to 1% of OLUMIANT 2 mg and Baricitinib 4 mg Treated Patients in Placebo-Controlled Trials for Rheumatoid Arthritis
Events | Weeks 0-16
Events | Placebo | OLUMIANT 2 mg | Baricitinib 4 mg
Events | n=1070 (%) | n=479 (%) | n=997 (%)
Upper respiratory tract infectionsa | 11.7 | 16.3 | 14.7
Nausea | 1.6 | 2.7 | 2.8
Herpes simplexb | 0.7 | 0.8 | 1.8
Herpes zoster | 0.4 | 1.0 | 1.4
a Includes acute sinusitis, acute tonsillitis, chronic tonsillitis, epiglottitis, laryngitis, nasopharyngitis, oropharyngeal pain, pharyngitis, pharyngotonsillitis, rhinitis, sinobronchitis, sinusitis, tonsillitis, tracheitis, and upper respiratory tract infection.
b Includes eczema herpeticum, genital herpes, herpes simplex, ophthalmic herpes simplex, and oral herpes.

Additional adverse drug reactions occurring in fewer than 1% of patients: acne.

Adverse Reactions in Patients with COVID-19

The safety of OLUMIANT was evaluated in two randomized, double-blind, placebo-controlled clinical trials of hospitalized adults with COVID-19 for up to 29 days, in which 1307 patients received at least one dose of OLUMIANT 4 mg once daily, and 1310 patients received placebo, for up to 14 days or until hospital discharge, whichever occurred first. In these studies, prophylaxis for venous thromboembolic event (VTEs) was recommended or required for all patients unless a major contraindication was noted.

Overall, the safety profile observed in patients with COVID-19 treated with OLUMIANT was consistent with the safety profile in patients with rheumatoid arthritis.

Overall Infections – During the first 29 days of the randomized clinical trials, infections were reported in 194 patients (14.8%) treated with OLUMIANT 4 mg and by 219 patients (16.7%) treated with placebo. The most commonly reported infection with OLUMIANT was pneumonia (3.1%).

Serious Infections – During the first 29 days of the randomized clinical trials, serious infections were reported in 98 patients (7.5%) treated with OLUMIANT 4 mg and 120 patients (9.2%) treated with placebo. The most commonly reported serious infections with OLUMIANT were COVID-19 pneumonia (2.1%) and septic shock (2.1%).

Opportunistic Infections – During the first 29 days of the randomized clinical trials, opportunistic infections were reported in 12 patients (0.9%) treated with OLUMIANT 4 mg and 14 patients (1.1%) treated with placebo. Tuberculosis was reported in 1 patient (0.1%) treated with OLUMIANT 4 mg and 0 patients treated with placebo.

Venous Thrombosis Events - During the first 29 days of the randomized clinical trials, pulmonary embolism was reported in 20 patients (1.5%) treated with OLUMIANT 4 mg and 11 patients (0.8%) treated with placebo. Deep vein thrombosis was reported in 20 patients (1.5%) treated with OLUMIANT 4 mg and 18 patients (1.4%) treated with placebo.

Adverse drug reactions in greater than or equal to 1% of patients in trials for COVID-19 are summarized in Table 9.

Table 9: Adverse Reactions That Occurred in Greater Than or Equal to 1% of Patients Treated with OLUMIANT 4 mg During the First 29 Days in Placebo-Controlled Trials for COVID-19
 | Placebo N = 1310 n (%) | OLUMIANT 4 mg N = 1307 n (%)
ALT ≥3 x ULNa | 201(16.0) | 230 (18.1)
AST ≥3 x ULNa | 117 (9.4) | 149 (11.8)
Thrombocytosis >600,000 cells/mm3a | 34 (4.6) | 59 (7.9)
Creatine phosphokinase (CPK) >5 x ULNa, b | 38 (4.7) | 36 (4.5)
Neutropenia <1000 cells/mm3a | 22 (1.8) | 26 (2.2)
Deep vein thrombosis | 18 (1.4) | 20 (1.5)
Pulmonary embolism | 11 (0.8) | 20 (1.5)
Urinary tract infection | 13 (1.0) | 19 (1.5)
a As assessed by measured values within the clinical trial database. Frequencies are based on shifts from pre-treatment to post-treatment (with number at risk as the denominator), except for ALT and AST for which frequencies are based on observed elevation during treatment.
b Creatine phosphokinase frequencies presented in the table were available for a single trial (COVID II) in patients with COVID-19 and do not represent integrated data.

Adverse Reactions in Patients with Alopecia Areata

The safety of OLUMIANT was evaluated in two placebo-controlled trials in patients with severe alopecia areata. Patients were randomized to placebo (371 patients), OLUMIANT 2 mg (365 patients), or OLUMIANT 4 mg (540 patients). Of these, a total of 845 patients were treated with OLUMIANT for at least 1 year.

Table 10 summarizes adverse reactions that occurred at a frequency of at least 1% in patients treated with OLUMIANT 2 mg once daily or OLUMIANT 4 mg once daily and more frequently than in patients treated with placebo during the 36-week placebo-controlled period of the alopecia areata clinical trials.

Table 10: Adverse Reactions That Occurred in ≥1% of Patients Treated with OLUMIANT 2 mg or OLUMIANT 4 mg in Alopecia Areata Trials
Adverse Reaction | Weeks 0-36
Adverse Reaction | Placebo | OLUMIANT 2 mg | OLUMIANT 4 mg
Adverse Reaction | N=371 (%) a | N=365 (%) a | N=540 (%) a
Upper respiratory tract infectionsb (URTI) | 19.9 | 18.4 | 21.3
Headache | 5.4 | 5.5 | 6.6
Acnec | 2.2 | 5.8 | 5.9
Hyperlipidemiad | 3.0 | 3.6 | 5.9
Blood creatine phosphokinase increased | 1.3 | 0.8 | 4.3
Urinary tract infections (UTI)e | 2.2 | 3.8 | 3.7
Liver enzyme elevationsf | 2.4 | 1.1 | 3.0
Folliculitisg | 0.8 | 1.4 | 2.2
Fatigue | 1.1 | 0.8 | 2.2
Lower respiratory tract infections (LRTI)h | 0.8 | 2.2 | 2.0
Nausea | 1.6 | 2.7 | 2.0
Genital Candida infectionsi | 0.3 | 2.2 | 1.3
Anemia | 0.3 | 0.3 | 1.3
Neutropeniaj | 0.8 | 0.3 | 1.3
Abdominal paink | 2.2 | 3.8 | 0.9
Herpes zoster | 0.5 | 1.4 | 0.9
Weight increased | 0.3 | 1.6 | 0.9
a %-study size adjusted percentages.
b URTI includes: acute sinusitis, influenza, laryngitis, nasopharyngitis, oropharyngeal pain, pharyngitis, pharyngotonsillitis, rhinitis, sinusitis, tonsillitis, upper respiratory tract infection, viral upper respiratory tract infection, viral sinusitis, viral pharyngitis, respiratory tract infection viral, rhinovirus infection and adenoiditis
c Acne includes: acne and dermatitis acneiform.
d Hyperlipidemia includes: hyperlipidaemia, hypercholesterolaemia, hypertriglyceridaemia, dyslipidaemia, lipids increased, low density lipoprotein increased, blood cholesterol increased, and blood triglycerides increased.
e UTI includes: cystitis, urinary tract infection, white blood cells urine positive, urinary tract infection bacterial, and pyelonephritis.
f Liver enzyme elevations includes: transaminases increased, aspartate aminotransferase increased, alanine aminotransferase increased, hepatic enzyme increased, gamma-glutamyl transferase increased, and hepatic function abnormal.
g Folliculitis was most commonly localized in the scalp region associated with hair regrowth
h LRTI includes: bronchitis, bronchiolitis, lower respiratory tract infection, pneumonia, COVID-19 pneumonia, and respiratory tract infection.
i Genital Candida infections includes: vulvovaginal candidiasis, vulvovaginal mycotic infection, and genital infection fungal.
j Neutropenia includes: neutropenia and neutrophil count decreased.
k Abdominal pain includes: abdominal pain, abdominal pain lower, abdominal pain upper, and abdominal discomfort.

In patients treated with any dose of baricitinib, adverse reactions that occurred in fewer than 1% of patients include arterial thrombosis, B cell lymphoma, lymphopenia, and fungal skin infections.

Additional adverse reactions observed after Week 52: venous thromboembolic events (VTE), including deep venous thrombosis (DVT) and pulmonary embolism (PE), and malignancy including non-melanoma skin cancer.

Overall, the adverse reactions observed in patients with alopecia areata treated with OLUMIANT were consistent with the adverse reactions in patients with rheumatoid arthritis.

6.2 Postmarketing Experience

The following adverse reactions have been identified during post-approval use of OLUMIANT. Because these reactions are reported voluntarily from a population of uncertain size, it is not always possible to reliably estimate their frequency or establish a causal relationship to drug exposure:

Immune System Disorders: Drug hypersensitivity (events such as rash, urticaria, and angioedema have been reported) [see Warnings and Precautions (5.6)].

7 DRUG INTERACTIONS

7.1 Strong OAT3 Inhibitors

Baricitinib exposure is increased when OLUMIANT is co-administered with strong OAT3 inhibitors (such as probenecid), hence the dosage of baricitinib should be reduced by half the recommended dose [see Dosage and Administration (2.2, 2.3) and Clinical Pharmacology (12.3)].

7.2 Other JAK Inhibitors or Biologic DMARDs

OLUMIANT has not been studied in combination with other JAK inhibitors or with biologic DMARDs [see Indications and Usage (1.1, 1.2)].

8 USE IN SPECIFIC POPULATIONS

8.1 Pregnancy

Risk Summary

Based on the findings from animal reproduction studies, OLUMIANT may cause fetal harm during pregnancy. Available data from clinical trials and postmarketing case reports with OLUMIANT exposure in pregnancy are insufficient to inform a drug-associated risk for major birth defects, miscarriage, or other adverse maternal or fetal outcomes. There are no human data on chronic baricitinib exposure throughout pregnancy. There are risks to the mother and the fetus associated with rheumatoid arthritis in pregnancy (see Clinical Considerations). Consider the risks and benefits with chronic use of OLUMIANT during pregnancy.

In animal embryo-fetal development studies, oral baricitinib administration to pregnant rats and rabbits at exposures equal to and greater than approximately 11 and 46 times the maximum recommended human dose (MRHD) of 4 mg/day, respectively, resulted in reduced fetal body weights, increased embryolethality (rabbits only), and dose-related increases in skeletal malformations. No developmental toxicity was observed in pregnant rats and rabbits treated with oral baricitinib during organogenesis at approximately 2 and 7 times the exposure at the MRHD, respectively. In a pre- and post-natal development study in pregnant female rats, oral baricitinib administration at exposures approximately 24 times the MRHD resulted in reduction in pup viability (increased incidence of stillborn pups and early neonatal deaths), decreased fetal birth weight, reduced fetal body weight gain, decreased cytotoxic T cells on post-natal day (PND) 35 with evidence of recovery by PND 65, and developmental delays that might be attributable to decreased body weight gain. No developmental toxicity was observed at an exposure approximately 5 times the exposure at the MRHD (see Data).

The background risks of major birth defects and miscarriage for the indicated population(s) are unknown. All pregnancies have a background risk of birth defect, loss, or other adverse outcomes. In the U.S. general population, the estimated background risk of major birth defects and miscarriage in clinically recognized pregnancies is 2-4% and 15-20%, respectively.

Report pregnancies to Eli Lilly and Company at 1-800-LillyRx (1-800-545-5979).

Clinical Considerations

Disease-Associated Maternal and/or Embryo/Fetal Risk

Published data suggest that increased disease activity is associated with the risk of developing adverse pregnancy outcomes in women with rheumatoid arthritis. Adverse pregnancy outcomes include preterm delivery (before 37 weeks of gestation), low birth weight (less than 2500 g) infants, and small for gestational age at birth.

Data

Animal Data

In an embryofetal development study in pregnant rats, dosed orally during the period of organogenesis from gestation days 6 to 17, baricitinib was teratogenic (skeletal malformations that consisted of bent limb bones and rib anomalies) at exposures equal to or greater than approximately 11 times the MRHD (on an AUC basis at maternal oral doses of 10 mg/kg/day and higher). No developmental toxicity was observed in rats at an exposure approximately 2 times the MRHD (on an AUC basis at a maternal oral dose of 2 mg/kg/day).

In an embryofetal development study in pregnant rabbits, dosed orally during the period of organogenesis from gestation days 7 to 20, embryolethality, decreased fetal body weights, and skeletal malformations (rib anomalies) were observed in the presence of maternal toxicity at an exposure approximately 46 times the MRHD (on an AUC basis at a maternal oral dose of 30 mg/kg/day). Embryolethality consisted of increased post-implantation loss that was due to elevated incidences of both early and late resorptions. No developmental toxicity was observed in rabbits at an exposure approximately 7 times the MRHD (on an AUC basis at a maternal oral dose of 10 mg/kg/day).

In a pre- and post-natal development study in pregnant female rats dosed orally from gestation day 6 through lactation day 20, adverse findings observed in pups included decreased survival from birth to post-natal day 4 (due to increased stillbirths and early neonatal deaths), decreased birth weight, decreased body weight gain during the pre-weaning phase, increased incidence of malrotated forelimbs during the pre-weaning phase, and decreased cytotoxic T cells on PND 35 with recovery by PND 65 at exposures approximately 24 times the MRHD (on an AUC basis at a maternal oral dose of 25 mg/kg/day). Developmental delays (that may be secondary to decreased body weight gain) were observed in males and females at exposures approximately 24 times the MRHD (on an AUC basis at a maternal oral dose of 25 mg/kg/day). These findings included decreased forelimb and hindlimb grip strengths, and delayed mean age of sexual maturity. No developmental toxicity was observed in rats at an exposure approximately 5 times the MRHD (on an AUC basis at a maternal oral dose of 5 mg/kg/day).

8.2 Lactation

Risk Summary

No information is available on the presence of OLUMIANT in human milk, the effects of the drug on the breastfed infant, or the effects of the drug on milk production. Baricitinib is present in the milk of lactating rats (see Data). Because of the potential for serious adverse reactions in nursing infants advise women not to breastfeed during treatment with OLUMIANT and for 4 days after the last dose (approximately 5 to 6 elimination half-lives).

Data

A single oral dose of 25 mg/kg radiolabeled baricitinib was administered to lactating female Sprague-Dawley rats on post-partum day 13. Drug exposure was approximately 45-fold greater in milk than in plasma based on AUC0-t values.

8.3 Females and Males of Reproductive Potential

Contraception

Based on animal studies, OLUMIANT may cause fetal harm when administered during pregnancy [see Use in Specific Populations (8.1)]. Consider pregnancy planning and prevention for females of reproductive potential.

8.4 Pediatric Use

The safety and effectiveness of OLUMIANT in pediatric patients have not been established.

8.5 Geriatric Use

Of the 3100 patients treated in the rheumatoid arthritis clinical trials, a total of 537 patients were 65 years of age and older, including 71 patients 75 years of age and older. Of the 2558 patients treated in the COVID-19 clinical trials, a total of 791 were 65 years of age and older, including 295 patients 75 years and older. No overall differences in safety or effectiveness were observed between these subjects and younger subjects, and other reported clinical experience has not identified differences in responses between the elderly and younger patients, but greater sensitivity of some older individuals cannot be ruled out [see Clinical Pharmacology (12.3)].

Of the 1200 patients in the alopecia areata clinical trials, a total of 29 patients were 65 years of age or older. The number of patients aged 65 years and older was not sufficient to determine whether they respond differently from younger patients.

OLUMIANT is known to be substantially excreted by the kidney, and the risk of adverse reactions to this drug may be greater in patients with impaired renal function. Because geriatric patients are more likely to have decreased renal function, care should be taken in dose selection, and it may be useful to monitor renal function [see Dosage and Administration (2.6)].

8.6 Hepatic Impairment

No dose adjustment is necessary in patients with mild or moderate hepatic impairment.

The use of OLUMIANT has not been studied in patients with rheumatoid arthritis or alopecia areata and severe hepatic impairment and is therefore not recommended. OLUMIANT has not been studied in patients with COVID-19 and severe hepatic impairment. OLUMIANT should only be used in patients with COVID-19 and severe hepatic impairment if the potential benefit outweighs the potential risk [see Dosage and Administration (2.6) and Clinical Pharmacology (12.3)].

8.7 Renal Impairment

Renal function was found to significantly affect baricitinib exposure.

Rheumatoid Arthritis and Alopecia Areata - The recommended dosage of OLUMIANT in patients with moderate renal impairment (estimated glomerular filtration rate (GFR) between 30 and <60 mL/min/1.73 m^2) should be reduced by half the recommended dose. OLUMIANT is not recommended for use in patients with rheumatoid arthritis or alopecia areata and severe renal impairment (estimated GFR of less than 30 mL/min/1.73 m^2) [see Dosage and Administration (2.6) and Clinical Pharmacology (12.3)].

COVID-19 - The recommended dosage of OLUMIANT in patients with moderate renal impairment (estimated GFR between 30 and <60 mL/min/1.73^2) or severe renal impairment (estimated GFR between 15 and <30 mL/min/1.73 m^2) is 2 mg once daily and 1 mg once daily, respectively. OLUMIANT is not recommended for use in patients who are on dialysis, have end-stage renal disease (ESRD), or with estimated GFR of <15 mL/min/1.73 m^2 [see Dosage and Administration (2.6) and Clinical Pharmacology (12.3)].

10 OVERDOSAGE

Single doses up to 40 mg and multiple doses of up to 20 mg daily for 10 days have been administered in clinical trials without dose-limiting toxicity. Pharmacokinetic data of a single dose of 40 mg in healthy volunteers indicate that more than 90% of the administered dose is expected to be eliminated within 24 hours.

In case of an overdose, it is recommended that the patient should be monitored for signs and symptoms of adverse reactions. Patients who develop adverse reactions should receive appropriate treatment.

11 DESCRIPTION

OLUMIANT (baricitinib) is a Janus kinase (JAK) inhibitor with the chemical name {1-(ethylsulfonyl)-3-[4-(7H-pyrrolo[2,3-d]pyrimidin-4-yl)-1H-pyrazol-1-yl]azetidin-3-yl}acetonitrile. Baricitinib has an empirical formula of C16H17N7O2S and a molecular weight of 371.42. Baricitinib has the following structural formula:

OLUMIANT tablets contain a recessed area on each face of the tablet surface and are available for oral administration as debossed, film-coated tablets. The 1 mg tablet is very light pink, round, debossed with “Lilly” on one side and “1” on the other. The 2 mg tablet is light pink, oblong, debossed with “Lilly” on one side and “2” on the other. The 4 mg tablet is medium pink, round, debossed with “Lilly” on one side and “4” on the other.

Each tablet contains 1, 2, or 4 mg of baricitinib and the following inactive ingredients: croscarmellose sodium, ferric oxide, lecithin (soya), magnesium stearate, mannitol, microcrystalline cellulose, polyethylene glycol, polyvinyl alcohol, talc and titanium dioxide.

12 CLINICAL PHARMACOLOGY

12.1 Mechanism of Action

Baricitinib is a Janus kinase (JAK) inhibitor. JAKs are intracellular enzymes which transmit signals arising from cytokine or growth factor-receptor interactions on the cellular membrane to influence cellular processes of hematopoiesis and immune cell function. Within the signaling pathway, JAKs phosphorylate and activate Signal Transducers and Activators of Transcription (STATs) which modulate intracellular activity including gene expression. Baricitinib modulates the signaling pathway at the point of JAKs, preventing the phosphorylation and activation of STATs.

JAK enzymes transmit cytokine signaling through their pairing (e.g., JAK1/JAK2, JAK1/JAK3, JAK1/TYK2, JAK2/JAK2, JAK2/TYK2). In cell-free isolated enzyme assays, baricitinib had greater inhibitory potency at JAK1, JAK2 and TYK2 relative to JAK3. In human leukocytes, baricitinib inhibited cytokine induced STAT phosphorylation mediated by JAK1/JAK2, JAK1/JAK3, JAK1/TYK2, or JAK2/TYK2 with comparable potencies. However, the relevance of inhibition of specific JAK enzymes to therapeutic effectiveness is not currently known.

12.2 Pharmacodynamics

Baricitinib inhibition of IL-6 induced STAT3 phosphorylation – Baricitinib administration resulted in a dose dependent inhibition of IL-6 induced STAT3 phosphorylation in whole blood from healthy subjects with maximal inhibition observed approximately 1 hour after dosing, which returned to near baseline by 24 hours. Similar levels of inhibition were observed using either IL-6 or TPO as the stimulus.

Immunoglobulins – Mean serum IgG, IgM, and IgA values decreased by 12 weeks after starting treatment with OLUMIANT, and remained stable through at least 52 weeks. For most patients, changes in immunoglobulins occurred within the normal reference range.

C-reactive protein – In patients with rheumatoid arthritis, decreases in serum C-reactive protein (CRP) were observed as early as one week after starting treatment with OLUMIANT and were maintained throughout dosing.

Cardiac Electrophysiology – At a dose 10 times the maximum recommended dose, baricitinib does not prolong the QT interval to any clinically relevant extent.

12.3 Pharmacokinetics

Following oral administration of OLUMIANT, peak plasma concentrations are reached approximately at 1 hour. A dose-proportional increase in systemic exposure was observed in the therapeutic dose range. The pharmacokinetics of baricitinib do not change over time. Steady-state concentrations are achieved in 2 to 3 days with minimal accumulation after once-daily administration.

Absorption – The absolute bioavailability of baricitinib is approximately 80%. An assessment of food effects in healthy subjects showed that a high-fat meal decreased the mean AUC and Cmax of baricitinib by approximately 11% and 18%, respectively, and delayed the tmax by 0.5 hours. Administration with meals is not associated with a clinically relevant effect on exposure. In clinical studies, OLUMIANT was administered without regard to meals.

Distribution – After intravenous administration, the volume of distribution is 76 L, indicating distribution of baricitinib into tissues. Baricitinib is approximately 50% bound to plasma proteins and 45% bound to serum proteins. Baricitinib is a substrate of the Pgp, BCRP, OAT3 and MATE2-K transporters, which play roles in drug distribution.

Elimination

Rheumatoid Arthritis and Alopecia Areata: The total body clearance of baricitinib is 8.9 L/h in patients with rheumatoid arthritis and 11 L/h in patients with alopecia areata. Elimination half-life in patients with rheumatoid arthritis and alopecia areata is approximately 12 to 16 hours.

COVID-19: The total body clearance and half-life of baricitinib is 14.2 L/h and 10.8 hours, respectively, in patients with COVID-19 who are intubated and have baricitinib administered via NG or OG tube.

Metabolism – Approximately 6% of the orally administered baricitinib dose is identified as metabolites (three from urine and one from feces), with CYP3A4 identified as the main metabolizing enzyme. No metabolites of baricitinib were quantifiable in plasma.

Excretion – Renal elimination is the principal clearance mechanism for baricitinib through filtration and active secretion as baricitinib is identified as a substrate of OAT3, Pgp, BCRP and MATE2-K from in vitro studies. In a clinical pharmacology study, approximately 75% of the administered dose was eliminated in the urine, while about 20% of the dose was eliminated in the feces. Baricitinib was excreted predominately as unchanged drug in urine (69%) and feces (15%).

Specific Populations

Effects of Body Weight, Gender, Race, and Age

Body weight, gender, race, ethnicity, and age did not have a clinically relevant effect on the PK (AUC and Cmax) of baricitinib (Figure 1). The mean effects of intrinsic factors on PK parameters (AUC and Cmax) were generally within the inter-subject PK variability of baricitinib. The inter-subject variabilities (% coefficients of variation) in AUC and Cmax of baricitinib are approximately 41% and 22%, respectively, in patients with rheumatoid arthritis [see Use in Specific Populations (8.5)].

Patients with Renal Impairment

Baricitinib systemic exposure in AUC was increased by 1.41-, 2.22-, 4.05- and 2.41-fold for mild, moderate, severe, and ESRD (with hemodialysis) renal impairment sub-groups, respectively, compared to subjects with normal renal function. The corresponding values for increase in Cmax were 1.16-, 1.46-, 1.40- and 0.88-fold, respectively (Figure 1) [see Use in Specific Populations (8.7)].

Patients with Hepatic Impairment

Baricitinib systemic exposure and Cmax increased by 1.19- and 1.08-fold for the moderate hepatic impairment group, respectively, compared to subjects with normal hepatic function (Figure 1) [see Use in Specific Populations (8.6)].

Figure 1: Impact of Intrinsic Factors on Baricitinib Pharmacokineticsa, b

a Reference values for weight, age, gender, and race comparisons are 70 kg, 54 years, male, and white, respectively; reference groups for renal and hepatic impairment are subjects with normal renal and hepatic function, respectively.

b Effects of renal and hepatic impairment on baricitinib exposure were summarized from dedicated renal and hepatic impairment studies, respectively. Effects of other intrinsic factors on baricitinib exposure were summarized from population PK analysis.

c The recommended dose for patients with COVID-19 and severe renal impairment (eGFR 15 - <30 mL/min/1.73m^2) is 1 mg once daily. OLUMIANT is not recommended for use in patients with COVID-19 who are on dialysis, have end-stage renal disease (ESRD), or acute kidney injury (eGFR <15 mL/min/1.73m^2). [see Dosage and Administration (2.6)]

Drug Interactions

Potential for Baricitinib to Influence the PK of Other Drugs

In vitro, baricitinib did not significantly inhibit or induce the activity of cytochrome P450 enzymes (CYPs 3A, 1A2, 2B6, 2C8, 2C9, 2C19, and 2D6). In clinical pharmacology studies, there were no clinically meaningful changes in the pharmacokinetics (PK) of simvastatin, ethinyl estradiol, or levonorgestrel (CYP3A substrates) when co-administered with baricitinib.

In vitro studies suggest that baricitinib is not an inhibitor of the transporters, P-glycoprotein (Pgp) or Organic Anion Transporting Polypeptide (OATP) 1B1. In vitro data indicate baricitinib does inhibit organic anionic transporter (OAT) 1, OAT2, OAT3, organic cationic transporter (OCT) 1, OCT2, OATP1B3, Breast Cancer Resistance Protein (BCRP) and Multidrug and Toxic Extrusion Protein (MATE) 1 and MATE2-K, but clinically meaningful changes in the pharmacokinetics of drugs that are substrates for these transporters are unlikely. In clinical pharmacology studies there were no clinically meaningful effects on the PK of digoxin (Pgp substrate) or methotrexate (substrate of several transporters) when co-administered with baricitinib.

Exposure changes of drugs following co-administration with baricitinib are shown in Figure 2.

Figure 2: Impact of Baricitinib on the Pharmacokinetics of Other Drugsa

a Reference group is administration of concomitant drug alone.

Potential for Other Drugs to Influence the PK of Baricitinib

In vitro studies suggest that baricitinib is a CYP3A4 substrate. In clinical pharmacology studies there was no effect on the PK of baricitinib when co-administered with ketoconazole (CYP3A inhibitor). There were no clinically meaningful changes in the PK of baricitinib when co-administered with fluconazole (CYP3A/CYP2C19/CYP2C9 inhibitor) or rifampicin (CYP3A inducer).

In vitro studies suggest that baricitinib is a substrate for OAT3, Pgp, BCRP and MATE2-K. In a clinical study, probenecid administration (strong OAT3 inhibitor) resulted in an approximately 2-fold increase in baricitinib AUC0-∞ with no effect on Cmax and tmax [see Dosage and Administration (2.2, 2.3) and Drug Interactions (7.1)]. However, simulations with diclofenac and ibuprofen (OAT3 inhibitors with less inhibition potential) predicted minimal effect on the PK of baricitinib. In clinical pharmacology studies there was no clinically meaningful effect on the PK of baricitinib when co-administered with cyclosporine (Pgp and BCRP inhibitor). Co-administration with methotrexate (substrate of several transporters) did not have a clinically meaningful effect on the PK of baricitinib.

Exposure changes of baricitinib following co-administration with CYP inhibitors or inducers, transporter inhibitors, as well as methotrexate and the proton pump inhibitor, omeprazole, are shown in Figure 3.

Figure 3: Impact of Other Drugs on the Pharmacokinetics of Baricitinibb

a Values are based on simulated studies.

b Reference group is administration of baricitinib alone.

13 NONCLINICAL TOXICOLOGY

13.1 Carcinogenesis, Mutagenesis, Impairment of Fertility

The carcinogenic potential of baricitinib was evaluated in Sprague-Dawley rats and Tg.rasH2 mice. No evidence of tumorigenicity was observed in male or female rats that received baricitinib for 91 to 94 weeks at oral doses up to 8 or 25 mg/kg/day, respectively (approximately 7 and 30 times the MRHD on an AUC basis). No evidence of tumorigenicity was observed in Tg.rasH2 mice that received baricitinib for 26 weeks at oral doses up to 300 and 150 mg/kg/day in male and female mice, respectively.

Baricitinib tested negative in the following genotoxicity assays: the in vitro bacterial mutagenicity assay (Ames assay), in vitro chromosome aberration assay in human peripheral blood lymphocytes, and in vivo rat bone marrow micronucleus assay.

Fertility (achievement of pregnancy) was reduced in male and female rats that received baricitinib at oral doses of 50 and 100 mg/kg/day respectively (approximately 62 and 93 times the MRHD in males and females, respectively, on an AUC basis) based upon findings that 7 of 19 (36.8%) drug-treated females with evidence of mating were not gravid compared to 1 of 19 (5.3%) control females. It could not be determined from the study design if these findings were attributable to toxicities in one sex or both. Fertility was unaffected in male and female rats at oral doses of 15 mg/kg and 25 mg/kg, respectively (approximately 13 and 26 times the MRHD on an AUC basis). However, maintenance of pregnancy was adversely affected at these doses based upon findings of increased post-implantation losses (early resorptions) and decreased numbers of mean viable embryos per litter. The number of viable embryos was unaffected in female rats that received baricitinib at an oral dose of 5 mg/kg/day and were mated to males that received the same dose (approximately 6 times the MRHD on an AUC basis). Reproductive performance was unaffected in male and female rats that received baricitinib at oral doses up to 50 and 100 mg/kg/day respectively (approximately 62 and 93 times the MRHD in males and females, respectively, on an AUC basis).

14 CLINICAL STUDIES

14.1 Rheumatoid Arthritis

The OLUMIANT clinical development program included two dose-ranging trials and four confirmatory phase 3 trials in patients with rheumatoid arthritis (RA). Although other doses have been studied, the recommended dosage of OLUMIANT is 2 mg once daily.

Dose-Ranging Studies

The dose-ranging studies RA-1 (NCT01185353) and RA-2 (NCT01469013) included a 12-week randomized comparison of baricitinib 1, 2, 4, and 8 mg orally once daily versus placebo in 301 and 145 patients, respectively.

The results from the dose-ranging studies are shown in Table 11. In dose-ranging Study RA-1, the observed ACR response was similar for baricitinib 1 and 2 mg daily and for baricitinib 4 and 8 mg daily, with the highest response for baricitinib 8 mg daily. In dose-ranging Study RA-2, there was not a clear trend of dose response, with similar response rates for 1 mg and 4 mg and 2 mg and 8 mg.

Table 11: Proportion of Patients with ACR20 Response at Week 12 in Dose-Ranging RA Studies
 | % ACR20 Responders
Dose-Ranging Study | Placebo | Baricitinib 1 mg daily | Baricitinib 2 mg daily | Baricitinib 4 mg daily | Baricitinib 8 mg daily
RA-1 (N=301) | 41 | 57 | 54 | 75 | 78
RA-2 (N=145) | 31 | 67 | 83 | 67 | 88

Confirmatory Studies

The efficacy and safety of OLUMIANT 2 mg once daily was assessed in two confirmatory phase 3 trials. These trials were randomized, double-blind, multicenter studies in patients with active rheumatoid arthritis diagnosed according to American College of Rheumatology (ACR)/European League Against Rheumatism 2010 criteria. Patients over 18 years of age were eligible if at least 6 tender and 6 swollen joints were present at baseline. The two studies (Studies RA-3 and RA-4) evaluated OLUMIANT 2 mg and baricitinib 4 mg.

Study RA-3 (NCT01721057) was a 24-week trial in 684 patients with moderately to severely active rheumatoid arthritis who had an inadequate response or intolerance to conventional DMARDs (cDMARDs). Patients received OLUMIANT 2 mg or 4 mg once daily or placebo added to existing background cDMARD treatment. From Week 16, non-responding patients could be rescued to receive baricitinib 4 mg once daily. The primary endpoint was the proportion of patients who achieved an ACR20 response at Week 12.

Study RA-4 (NCT01721044) was a 24-week trial in 527 patients with moderately to severely active rheumatoid arthritis who had an inadequate response or intolerance to 1 or more TNF inhibitor therapies with or without other biologic DMARDs (TNFi-IR). Patients received OLUMIANT 2 mg or baricitinib 4 mg once daily or placebo added to background cDMARD treatment. From Week 16, non-responding patients could be rescued to receive baricitinib 4 mg once daily. The primary endpoint was the proportion of patients who achieved an ACR20 response at Week 12.

Clinical Response

The percentages of OLUMIANT-treated patients achieving ACR20, ACR50, and ACR70 responses, and Disease Activity Score (DAS28-CRP) <2.6 in Studies RA-3 and RA-4 are shown in Table 8.

Patients treated with OLUMIANT had higher rates of ACR response and DAS28-CRP <2.6 versus placebo-treated patients at Week 12 (Studies RA-3 and RA-4) (Table 12).

In Study RA-4, higher ACR20 response rates (Figure 4) were observed as early as 1 week with OLUMIANT 2 mg versus placebo.

In Study RA-4, the proportions of patients achieving DAS28-CRP <2.6 who had at least 3 active joints at the end of Week 24 were 18.2% and 10.5%, in the placebo and OLUMIANT 2 mg arms, respectively.

Table 12: Clinical Response in RA Studies RA-3 and RA-4a
 | Percent of Patients
 | cDMARD-IR |  | TNFi-IR
 | Study RA-3 |  | Study RA-4
 | Placebo + cDMARDs | OLUMIANT 2 mg/day + cDMARDs ∆ (95% CI) b | Placebo + cDMARDs | OLUMIANT 2 mg/day + cDMARDs ∆ (95% CI) b
N | 228 | 229 | 176 | 174
ACR 20
Week 12 % | 39 | 66 27 (18, 35) | 27 | 49 22 (12, 32)
Week 24 % | 42 | 61 19 (10, 28) | 27 | 45 18 (8, 27)
ACR 50
Week 12 % | 13 | 34 21 (13, 28) | 8 | 20 12 (5, 19)
Week 24 % | 21 | 41 20 (12, 28) | 13 | 23 10 (2, 18)
ACR 70
Week 12 % | 3 | 18 15 (9, 20) | 2 | 13 11 (5, 16)
Week 24 % | 8 | 25 17 (11, 24) | 3 | 13 10 (4, 16)
DAS28-CRP<2.6
Week 12 % | 9 | 26 (10, 24) | 4 | 11 (2, 12)
Week 24 % | 11 | 31 (13, 27) | 6 | 11 (-1, 11)
a Patients who were rescued or discontinued treatment were considered as non-responders in the analyses.
b 95% confidence interval for the difference (∆) in response rate between OLUMIANT treatment and placebo (Study RA-3, Study RA-4).

The effects of OLUMIANT treatment on the components of the ACR response criteria for Studies RA-3 and RA-4 are shown in Table 13.

Table 13: Components of ACR Response at Week 12 in RA Studies RA-3 and RA-4a
 | cDMARD-IR |  | TNFi-IR
 | Study RA-3 |  | Study RA-4
 | Placebo + cDMARDs | OLUMIANT 2 mg/day + cDMARDs | Placebo + cDMARDs | OLUMIANT 2 mg/day + cDMARDs
N | 228 | 229 | 176 | 174
Number of Tender Joints (0-68)
Baseline | 24 (15) | 24 (14) | 28 (16) | 31 (16)
Week 12 | 15 (14) | 11 (13) | 20 (16) | 19 (18)
Number of Swollen Joints (0-66)
Baseline | 13 (7) | 14 (9) | 17 (11) | 19 (12)
Week 12 | 8 (8) | 5 (6) | 12 (10) | 10 (12)
Painb
Baseline | 57 (23) | 60 (21) | 65 (19) | 62 (22)
Week 12 | 43 (24) | 34 (25) | 55 (25) | 46 (28)
Patient Global Assessmentb
Baseline | 60 (21) | 62 (20) | 66 (19) | 67 (19)
Week 12 | 44 (23) | 36 (25) | 56 (25) | 46 (26)
Physician Global Assessmentb
Baseline | 62 (17) | 64 (17) | 67 (19) | 67 (17)
Week 12 | 41 (24) | 33 (22) | 50 (26) | 36 (24)
Disability Index (HAQ-DI) c
Baseline | 1.50 (0.60) | 1.51 (0.62) | 1.78 (0.57) | 1.71 (0.55)
Week 12 | 1.17 (0.62) | 0.96 (0.69) | 1.59 (0.68) | 1.31 (0.72)
hsCRP (mg/L)
Baseline | 17.7 (20.4) | 18.2 (21.5) | 20.6 (25.3) | 19.9 (22.5)
Week 12 | 17.2 (19.3) | 8.6 (14.6) | 19.9 (23.0) | 13.5 (20.1)
a Data shown are mean (standard deviation).
b Visual analog scale: 0=best, 100=worst.
c Health Assessment Questionnaire–Disability Index: 0=best, 3=worst; 20 questions; 8 categories: dressing and grooming, arising, eating, walking, hygiene, reach, grip, and activities.

Figure 4: Percent of RA Patients Achieving ACR20 in Study RA-4

Physical Function Response

Improvement in physical function was measured by the Health Assessment Questionnaire-Disability Index (HAQ-DI). Patients receiving OLUMIANT 2 mg demonstrated greater improvement from baseline in physical functioning compared to placebo at Week 24. The mean difference (95% CI) from placebo in HAQ-DI change from baseline at Week 24 was -0.24 (-0.35, -0.14) in Study RA-3 and -0.23 (-0.35, -0.12) in Study RA-4.

Other Health Related Outcomes

General health status was assessed by the Short Form health survey (SF-36). In Studies RA-3 and RA-4, compared to placebo, patients treated with OLUMIANT 2 mg demonstrated greater improvement from baseline in the physical component summary (PCS) score and the physical function, role physical, bodily pain, vitality, and general health domains at Week 12, with no consistent improvements in the mental component summary (MCS) scores or the role emotional, mental health, and social functioning domains.

14.2 COVID-19

The efficacy and safety of baricitinib were assessed in 2 Phase 3, randomized, double-blind, placebo-controlled clinical trials:

- COVID I (NCT04401579), which evaluated the combination of baricitinib 4 mg + remdesivir compared to placebo + remdesivir.
- COVID II (NCT04421027), which evaluated baricitinib 4 mg compared to placebo. Patients could remain on background therapy, as defined per local guidelines. An additional exploratory sub-study in patients requiring invasive mechanical ventilation or ECMO at baseline was also conducted under this protocol and analyzed separately.

COVID I

A randomized, double-blind, placebo-controlled clinical trial (NCT04401579) of hospitalized adults with confirmed SARS-CoV-2 infection compared treatment with baricitinib plus remdesivir (n = 515) with placebo plus remdesivir (n = 518). Patients had to have laboratory-confirmed SARS-CoV-2 infection as well as at least one of the following to be enrolled in the trial: radiographic infiltrates by imaging, SpO2 ≤94% on room air, a requirement for supplemental oxygen, or a requirement for mechanical ventilation or ECMO. Patients treated with the combination received the following regimen:

- Baricitinib 4 mg once daily (orally) for up to 14 days or until hospital discharge, whichever came first
- Remdesivir 200 mg on Day 1 and 100 mg once daily (via intravenous infusion) on subsequent days for a total treatment duration of 10 days or until hospital discharge

In this study prophylaxis for venous thromboembolic event (VTEs) was recommended for all patients unless a major contraindication was noted.

For the overall population (N = 1033 patients) at randomization, mean age was 55 years (with 30% of patients aged 65 or older); 63% of patients were male, 51% were Hispanic or Latino, 48% were White, 15% were Black or African American, and 10% were Asian; 14% did not require supplemental oxygen, 55% required supplemental oxygen, 21% required non-invasive ventilation or high-flow oxygen, and 11% required invasive mechanical ventilation or ECMO. The most common comorbidities were obesity (56%), hypertension (52%), and type 2 diabetes (37%). Demographics and disease characteristics were balanced across the combination group and the placebo group.

The primary endpoint, for the intent to treat population, was time to recovery within 29 days after randomization. Recovery was defined as being discharged from the hospital without limitations on activities, being discharged from the hospital with limitations on activities and/or requiring home oxygen or hospitalized but not requiring supplemental oxygen and no longer requiring medical care. The key secondary endpoint was clinical status on Day 15 assessed on an 8-point ordinal scale (OS) consisting of the following categories:

1. Not hospitalized, no limitations on activities [OS-1];
2. Not hospitalized, limitation on activities and/or requiring home oxygen [OS-2];
3. Hospitalized, not requiring supplemental oxygen - no longer requires ongoing medical care [OS-3];
4. Hospitalized, not requiring supplemental oxygen - requiring ongoing medical care (COVID-19 related or otherwise) [OS 4];
5. Hospitalized, requiring supplemental oxygen [OS 5];
6. Hospitalized, on non-invasive ventilation or high-flow oxygen devices [OS 6];
7. Hospitalized, on invasive mechanical ventilation or ECMO [OS 7]; and
8. Death [OS 8]

For the overall population, the median time to recovery (defined as discharged from hospital or hospitalized but not requiring supplemental oxygen or ongoing medical care) was 7 days for baricitinib + remdesivir compared to 8 days for placebo + remdesivir [hazard ratio: 1.16 (95% CI 1.01, 1.33); p = 0.035].

Patients assigned to baricitinib + remdesivir were more likely to have a better clinical status (according to an 8-point ordinal scale) at Day 15 compared to patients assigned to placebo + remdesivir [odds ratio: 1.26 (95% CI 1.01, 1.57); p = 0.044].

The proportion of patients who died or progressed to non-invasive ventilation/high-flow oxygen or invasive mechanical ventilation by Day 29 was lower in baricitinib + remdesivir (23%) compared to placebo + remdesivir (28%) [odds ratio: 0.74 (95% CI 0.56, 0.99); p = 0.039]. Patients who required non-invasive ventilation/high-flow oxygen or invasive mechanical ventilation (including ECMO) at baseline needed to worsen by at least 1 point on an 8-point ordinal scale to progress.

The proportion of patients who died by Day 29 was 4.7% (24/515) for baricitinib + remdesivir compared to 7.1% (37/518) for placebo + remdesivir [Kaplan Meier estimated difference in Day 29 probability of mortality: -2.6% (95% CI: -5.8%, 0.5%); hazard ratio = 0.65 (95% CI: 0.39, 1.09)].

COVID II

A randomized, double-blind, placebo-controlled clinical trial (NCT04421027) of hospitalized adults with confirmed SARS-CoV-2 infection compared treatment with baricitinib 4mg once daily (n = 764) with placebo (n = 761) for 14 days or hospital discharge, whichever came first. Patients could remain on background standard of care, as defined per local guidelines, including antimalarials, antivirals, corticosteroids, and/or azithromycin. In this study prophylaxis for venous thromboembolic event (VTE) was required for all patients unless contraindicated.

The most frequently used therapies at baseline were:

- corticosteroids (79% of patients, mostly dexamethasone)
- remdesivir (19% of patients)

Patients had to have laboratory-confirmed SARS-CoV-2 infection, at least one instance of elevation in at least one inflammatory marker above the upper limit of normal according to local laboratory ranges (CRP, D-dimer, LDH, ferritin), and at least one of the following to be enrolled in the trial: radiographic infiltrates by imaging, SpO2 <94% on room air, evidence of active COVID infection (with clinical symptoms including any of the following: fever, vomiting, diarrhea, dry cough, tachypnea defined as respiratory rate >24 breaths/min) or requirement for supplemental oxygen.

For the overall population (N = 1525 patients) at randomization, mean age was 58 years (with 33% of patients aged 65 or older); 63% of patients were male, 60% were White, 5% were Black or African American, 11% were Asian; 12% did not require supplemental oxygen (OS 4), 63% required supplemental oxygen (OS 5), 24% required non-invasive ventilation or high-flow oxygen (OS 6). The most common comorbidities were hypertension (48%), obesity (33%), and type 2 diabetes (29%). Demographics and disease characteristics were balanced across the baricitinib and placebo groups.

The primary endpoint was the proportion of patients who died or progressed to non-invasive ventilation/high-flow oxygen or invasive mechanical ventilation within the first 28-days of the study. Patients who required non-invasive ventilation/high-flow oxygen at baseline needed to worsen by at least 1 point on an 8-point OS to progress (refer to the description of COVID I for the definition of the 8-point OS). A key secondary endpoint was all-cause mortality by Day 28.

The estimated proportion of patients who died or progressed to non-invasive ventilation/high-flow oxygen or invasive mechanical ventilation was lower in patients treated with baricitinib (27.8%) compared to placebo (30.5%), but this effect was not statistically significant [odds ratio: 0.85 (95% CI 0.67, 1.08); p = 0.180].

The proportion of patients who died by Day 28 was 8.1% (62/764) for baricitinib compared to 13.3% (101/761) for placebo [estimated difference in Day 28 probability of mortality = -4.9% (95% CI: -8.0%, -1.9%); hazard ratio = 0.56 (95% CI: 0.41, 0.77)].

COVID II Exploratory Sub-Study

In a separate group of patients requiring invasive mechanical ventilation or ECMO at baseline and enrolled in an addendum to COVID II, a pre-specified exploratory analysis showed that the proportion who died by Day 28 was 39.2% (20/51) for baricitinib compared to 58.0% (29/50) for placebo [estimated difference in Day 28 risk of mortality = -18.8% (95% CI: -36.3%, 0.6%); hazard ratio = 0.54 (95% CI: 0.31, 0.96)].

14.3 Alopecia Areata

Two randomized, double-blind, placebo-controlled trials [Trials AA-1 (NCT03570749) and AA-2 (NCT03899259)] enrolled a total of 1200 patients, with alopecia areata (AA), who had at least 50% scalp hair loss as measured by the Severity of Alopecia Tool (SALT) for more than 6 months. The trials enrolled males 18 to 60 years of age and females 18 to 70 years of age. Among the patients enrolled, 61% were female, 2% were 65 years of age or older, and 52% were White, 36% were Asian, and 8% were Black. At baseline, 53% of patients had at least 95% scalp hair loss, 34% had their current episode lasting at least 4 years, 69% had significant gaps in eyebrow hair or no notable eyebrow hair, and 58% had significant gaps in eyelashes or no notable eyelashes.

In the Phase 3 portion of Trial AA-1 and in Trial AA-2, patients received OLUMIANT 2 mg, OLUMIANT 4 mg, or placebo once daily.

Both trials assessed the proportion of patients who achieved at least 80% scalp hair coverage (SALT score of ≤20) at Week 36 as the primary endpoint. Other outcomes at Week 36 included the proportion of patients who achieved at least 90% scalp hair coverage (SALT score of ≤10), patients with Scalp Hair Assessment PRO™ score of 0 or 1 with at least 2-point reduction on the 5-point scale, and assessments of eyebrow and eyelash hair loss.

Clinical Response

The results of the OLUMIANT trials (AA-1 and AA-2) are provided in Table 14 and Figure 5.

Table 14: Clinical Response at Week 36 in Patients with Severe AA
 | Trial AA-1 |  |  | Trial AA-2
 | Placebo | OLUMIANT 2 mg/day | OLUMIANT 4 mg/day | Placebo | OLUMIANT 2 mg/day | OLUMIANT 4 mg/day
Number of subjects with at least 50% scalp hair loss at baseline
N | 189 | 184 | 281 | 156 | 156 | 234
SALT ≤ 20 Difference from Placebo (95% CI) | 5% | 22% 16% (10, 23) | 35% 30% (23, 36) | 3% | 17% 15% (8, 22) | 32% 30% (23, 36)
SALT ≤ 10 Difference from Placebo (95% CI) | 4% | 13% 9% (3, 15) | 26% 22% (16, 28) | 1% | 11% 10% (5, 16)a | 24% 23% (17, 29)
Number of subjects reporting Scalp Hair Assessment PRO™ score ≥3 at baseline
N | 181 | 175 | 275 | 151 | 149 | 215
Scalp Hair Assessment PRO score of 0 or 1b Difference from Placebo (95% CI) | 5% | 16% 11% (5, 18) | 33% 28% (21, 34) | 4% | 16% 12% (5, 19) | 34% 30% (23, 37)
a Not statistically significant under the multiplicity control plan
b Patients evaluated scalp hair coverage on a 5-point scale where 0 = No missing hair (0% of scalp hair missing; full head of hair), 1 = A limited area of scalp hair loss (1% to 20%), 2 = moderate scalp hair loss (21% to 49%), 3 = a large area of scalp hair loss (50% to 94%), and 4 = nearly all or all scalp hair loss (95% to 100%).

Among patients with substantial eyebrow and eyelash hair loss at baseline, an improvement in eyebrow and eyelash coverage was observed on OLUMIANT 4 mg once daily dosage at Week 36.

Figure 5: Percent of Patients Achieving SALT ≤20

Analyses by age, gender, race, and body weight did not identify differences in response to 36-weeks of treatment with OLUMIANT among these subgroups. SALT ≤20 response rates were higher in all dose groups in patients with baseline SALT 50 to 94 versus SALT 95 to 100. See Table 15.

Table 15: SALT ≤20 at Week 36 by Baseline SALT Severity in AA
 | Trials AA-1 and AA-2
 | Placebo | OLUMIANT 2 mg/day | OLUMIANT 4 mg/day
50 % to 94% Scalp Hair Loss N SALT ≤20 | 166 8% | 147 33% | 248 48%
95 % to 100% Scalp Hair Loss N SALT ≤20 | 178 1% | 193 10% | 267 21%

In AA-2, patients who achieved adequate response (SALT ≤20) to OLUMIANT 4 mg once daily at 52 weeks of treatment entered a randomized down-titration period and received OLUMIANT 2 mg once daily or remained on OLUMIANT 4 mg once daily. After an additional 24 weeks of treatment (76 weeks total), 75% (30/40) of patients randomized to OLUMIANT 2 mg once daily maintained response and 98% (41/42) of patients who remained on OLUMIANT 4 mg once daily maintained response.

16 HOW SUPPLIED/STORAGE AND HANDLING

16.1 How Supplied

OLUMIANT for oral administration is available as debossed, film-coated, tablets. Each tablet contains a recessed area on each face of the tablet surface.

OLUMIANT Tablets | 1 mg | 2 mg | 4 mg
Color | Very Light Pink | Light Pink | Medium Pink
Shape | Round | Oblong | Round
Identification | Lilly | Lilly | Lilly
Identification | 1 | 2 | 4
NDC Codes
Bottle of 30 | 0002-4732-30 | 0002-4182-30 | 0002-4479-30

16.2 Storage and Handling

Store at 20°C to 25°C (68°F to 77°F); excursions permitted to 15°C to 30°C (59°F to 86°F) [see USP Controlled Room Temperature].

Keep out of reach of children.

17 PATIENT COUNSELING INFORMATION

Advise the patient to read the FDA-approved patient labeling (Medication Guide).

Infections

Inform patients that they may be more likely to develop infections when taking OLUMIANT. Instruct patients to tell their healthcare provider if they develop any signs or symptoms of an infection [see Warnings and Precautions (5.1)].

Advise patients that the risk of herpes zoster is increased in patients treated with OLUMIANT and some cases can be serious [see Warnings and Precautions (5.1)].

Malignancies and Lymphoproliferative Disorders

Inform patients that OLUMIANT may increase their risk of developing lymphomas and other malignancies, including of the skin and that periodic skin examinations should be performed while using OLUMIANT. Instruct patients to inform their healthcare provider if they have ever had any type of cancer [see Warnings and Precautions (5.3)].

Major Adverse Cardiovascular Events

Inform patients that OLUMIANT may increase their risk of major adverse cardiovascular events (MACE) including myocardial infarction, stroke, and cardiovascular death. Instruct all patients, especially current or past smokers or patients with other cardiovascular risk factors, to be alert for the development of signs and symptoms of cardiovascular events [see Warnings and Precautions (5.4)].

Thrombosis

Advise patients that events of DVT and PE have been reported in clinical studies with OLUMIANT. Instruct patients to seek immediate medical attention if they develop any signs or symptoms of a DVT or PE [see Warnings and Precautions (5.5)].

Hypersensitivity Reactions

Advise patients to discontinue OLUMIANT and seek immediate medical attention if they develop any signs and symptoms of serious allergic reactions [see Warnings and Precautions (5.6)].

Gastrointestinal Perforations

Inform patients that gastrointestinal perforations have been reported in clinical trials with OLUMIANT. Instruct patients to seek medical care immediately if they experience new onset of abdominal pain, fever, chills, nausea, or vomiting [see Warnings and Precautions (5.7)].

Laboratory Abnormalities

Inform patients that OLUMIANT may affect certain lab tests, and that blood tests are required before and during OLUMIANT treatment [see Warnings and Precautions (5.8)].

Live Vaccines

Instruct patients to inform the healthcare practitioner that they are taking OLUMIANT prior to a potential vaccination since the use of live vaccine is not recommended [see Warnings and Precautions (5.9)].

Pregnancy

Advise pregnant females and females of reproductive potential of the potential risk to a fetus and to inform their healthcare provider if they are pregnant or intend to become pregnant during treatment with OLUMIANT. Inform patients to report their pregnancy to Eli Lilly and Company at 1-800-LillyRx (1-800-545-5979) [see Use in Specific Populations (8.1, 8.3)].

Lactation

Advise a woman not to breastfeed during treatment with OLUMIANT and for four days after the last dose [see Use in Specific Populations (8.2)].

Literature revised: 06/2022

Marketed by: Lilly USA, LLC, Indianapolis, IN 46285, USA

www.olumiant.com

Copyright © 2018, 2022, Eli Lilly and Company. All rights reserved.

OLM-0007-USPI-20220613

MEDICATION GUIDE
OLUMIANT® (O-loo-me-ant)
(baricitinib)
tablets, for oral use

What is the most important information I should know about OLUMIANT?
OLUMIANT may cause serious side effects, including:
1. Serious infections.
OLUMIANT is a medicine that affects your immune system. OLUMIANT can lower the ability of your immune system to fight infections. Some people have had serious infections while taking OLUMIANT, including tuberculosis (TB), and infections caused by bacteria, fungi, or viruses that can spread throughout the body. Some people have died from these infections.

- Your healthcare provider should test you for TB before starting treatment with OLUMIANT for rheumatoid arthritis or alopecia areata.
- Your healthcare provider should watch you closely for signs and symptoms of TB during treatment with OLUMIANT.

You should not start taking OLUMIANT if you have any kind of infection unless your healthcare provider tells you it is okay. You may be at a higher risk of developing shingles.
Before starting OLUMIANT, tell your healthcare provider if you:

- are being treated for an infection
- have an infection that does not go away or that keeps coming back
- have diabetes, chronic lung disease, HIV, or a weak immune system. People with these conditions have a higher chance for infections
- have TB or have been in close contact with someone with TB
- have had shingles (herpes zoster)
- have had hepatitis B or C
- live or have lived, or have traveled to certain parts of the country (such as the Ohio and Mississippi River valleys and the Southwest) where there is an increased chance for getting certain kinds of fungal infections. These infections may happen or become more severe if you use OLUMIANT. Ask your healthcare provider if you do not know if you have lived in an area where these infections are common.
- think you have an infection or have symptoms of an infection such as:

- fever, sweating, or chills
- shortness of breath
- warm, red, or painful skin or sores on your body
- feeling tired

- muscle aches
- blood in your phlegm
- diarrhea or stomach pain

- cough
- weight loss
- burning when you urinate or urinating more often than normal

After starting OLUMIANT, call your healthcare provider right away if you have any symptoms of an infection. OLUMIANT can make you more likely to get infections or, make worse any infection that you have. If you get a serious infection, your healthcare provider may stop your treatment with OLUMIANT until your infection is controlled.
2. Increased risk of death in people 50 years of age and older who have at least 1 heart disease (cardiovascular) risk factor and are taking a medicine in the class of medicines called Janus kinase (JAK) inhibitors. OLUMIANT is a JAK inhibitor medicine.
3. Cancer and immune system problems.
OLUMIANT may increase your risk of certain cancers by changing the way your immune system works.

- Lymphoma and other cancers including skin cancers can happen in people taking OLUMIANT. People taking a medicine in the class of medicines called Janus kinase (JAK) inhibitors have a higher risk of certain cancers including lymphoma and lung cancer, especially if you are a current or past smoker.
- Tell your healthcare provider if you have ever had any type of cancer. Follow your healthcare provider's advice about having your skin checked for skin cancer during treatment with OLUMIANT.

4. Increased risk of major cardiovascular events such as heart attack, stroke or death in people 50 years of age and older who have at least 1 heart disease (cardiovascular) risk factor and taking a medicine in the class of medicines called JAK inhibitors, especially if you are a current or past smoker.
Get emergency help right away if you have any symptoms of a heart attack or stroke while taking OLUMIANT, including:

- discomfort in the center of your chest that lasts for more than a few minutes, or that goes away and comes back
- severe tightness, pain, pressure, or heaviness in your chest, throat, neck, or jaw
- pain or discomfort in your arms, back, neck, jaw, or stomach
- shortness of breath with or without chest discomfort
- breaking out in a cold sweat
- nausea or vomiting
- feeling lightheaded
- weakness in one part or on one side of your body
- slurred speech

5. Blood Clots.
Blood clots in the veins of your legs (deep vein thrombosis, DVT) or lungs (pulmonary embolism, PE) and arteries (arterial thrombosis) can happen in some people taking OLUMIANT. This may be life-threatening and cause death. Blood clots in the veins of the legs (deep vein thrombosis, DVT) and lungs (pulmonary embolism, PE) have happened more often in people who are 50 years of age and older and with at least 1 heart disease (cardiovascular) risk factor taking a medicine in the class of medicines called Janus kinase (JAK) inhibitors.

- Tell your healthcare provider if you have had blood clots in the veins of your legs or lungs in the past.
- Stop taking OLUMIANT and tell your healthcare provider or get emergency help right away if you have any signs and symptoms of blood clots during treatment with OLUMIANT, including: swelling, pain or tenderness in the leg, sudden unexplained chest pain, or shortness of breath.

6. Allergic Reactions.
Symptoms such as rash (hives), trouble breathing, feeling faint or dizzy, or swelling of your lips, tongue, or throat, that may mean you are having an allergic reaction have been seen in people taking OLUMIANT. Some of these reactions were serious. If any of these symptoms occur during treatment with OLUMIANT, stop taking OLUMIANT and get emergency help right away.

7. Tears (perforation) in the stomach or intestines.

- Tell your healthcare provider if you have had diverticulitis (inflammation in parts of the large intestine) or ulcers in your stomach or intestines. Some people taking OLUMIANT can get tears in their stomach or intestines. This happens most often in people who also take nonsteroidal anti-inflammatory drugs (NSAIDs), corticosteroids, or methotrexate.
- Tell your healthcare provider right away if you have fever and stomach-area pain that does not go away, and a change in your bowel habits.

8. Changes in certain laboratory test results.
Your healthcare provider should do blood tests before you start taking OLUMIANT and while you take OLUMIANT to check for the following:

- low neutrophil and lymphocyte counts. Neutrophils and lymphocytes are types of white blood cells that help the body fight off infections.
- low red blood cell counts. This may mean that you have anemia, which may make you feel weak and tired.
- increased cholesterol levels. If you are being treated for rheumatoid arthritis or alopecia areata, your healthcare provider should do blood tests to check your cholesterol levels approximately 12 weeks after you start taking OLUMIANT, and as needed.
- elevated liver enzymes. Liver enzymes help to tell if your liver is functioning normally. Elevated liver enzymes may indicate that your healthcare provider needs to do additional tests on your liver.

You should not take OLUMIANT if your lymphocyte count, neutrophil count, or red blood cell count is too low or your liver tests are too high. Your healthcare provider may stop your OLUMIANT treatment for a period of time if needed because of changes in these blood test results.
See "What are the possible side effects of OLUMIANT?" for more information about side effects.

What is OLUMIANT?
OLUMIANT is a prescription medicine that is a Janus Kinase (JAK) inhibitor. OLUMIANT is used to treat:

- adults with moderately to severely active rheumatoid arthritis after treatment with 1 or more medicines called tumor necrosis factor (TNF) blockers have been used and did not work well enough or could not be tolerated
- adult patients hospitalized with coronavirus disease 2019 (COVID-19) requiring oxygen or assistance with breathing.
- adults with severe alopecia areata

It is not known if OLUMIANT is safe and effective in children.

Before taking OLUMIANT, tell your healthcare provider about all your medical conditions, including if you:

- See “What is the most important information I should know about OLUMIANT?”
- have an infection
- are a current or past smoker
- have had a heart attack, other heart problems or stroke
- have kidney problems
- have liver problems
- have low red or white blood cell counts
- have recently received or are scheduled to receive a vaccine. People who take OLUMIANT should not receive live vaccines.
- have any stomach area (abdominal) pain or been diagnosed with diverticulitis or ulcers in your stomach or intestines
- are pregnant or plan to become pregnant. It is not known if OLUMIANT will harm an unborn baby. If you become pregnant during treatment with OLUMIANT call Eli Lilly and Company at 1-800-545-5979 to report the pregnancy.
- are breastfeeding or plan to breastfeed. It is not known if OLUMIANT passes into your breast milk. You should not breastfeed during treatment with OLUMIANT and for 4 days after the last dose. Talk to your healthcare provider about the best way to feed your baby during treatment with OLUMIANT.

Tell your healthcare provider about all the medicines you take, including prescription and over-the-counter medicines, vitamins, and herbal supplements.
OLUMIANT and other medicines may affect each other causing side effects.
Especially tell your healthcare provider if you take:

- a medicine called probenecid
- medicines that affect your immune system such as biologic medications, other JAK inhibitors, and strong immunosuppressants (such as azathioprine and cyclosporine) as these medicines may increase your risk of infection.

Ask your healthcare provider or pharmacist if you are not sure if you are taking one of these medicines.
Know the medicines you take. Keep a list of them to show your healthcare provider and pharmacist when you get a new medicine.

How should I take OLUMIANT?

- Take OLUMIANT exactly as your healthcare provider tells you to take it.
- For people with rheumatoid arthritis or alopecia areata, take OLUMIANT 1 time a day by mouth with or without food.
- For people with COVID-19, OLUMIANT will be given to you 1 time a day by mouth with or without food, for up to 14 days or until you are discharged from the hospital (whichever comes first), as instructed by your healthcare provider.
- Talk to your healthcare provider if you cannot swallow tablets whole.
- If you take too much OLUMIANT, call your healthcare provider or poison control center at 1-800-222-1222, or go to the nearest hospital emergency room right away.

What are the possible side effects of OLUMIANT?
OLUMIANT may cause serious side effects including:
See “What is the most important information I should know about OLUMIANT?”
The most common side effects of OLUMIANT in people treated for rheumatoid arthritis include:

- upper respiratory tract infections (common cold, sinus infections)
- nausea

- herpes simplex virus infections, including cold sores
- shingles (herpes zoster)

The most common side effects of OLUMIANT in people treated for COVID-19 include:

- increased liver enzyme levels
- increased platelets in your blood (thrombocytosis)
- increased blood creatine phosphokinase
- low white blood cell count (neutropenia)

- blood clots in the veins of your legs (DVT)
- blood clot in your lungs (pulmonary embolism)
- urinary tract infection

The most common side effects of OLUMIANT in people treated for alopecia areata include:

- upper respiratory tract infections (common cold, sinus infections)
- headache
- acne
- increased blood cholesterol
- increased blood creatine phosphokinase
- urinary tract infection
- increased liver enzyme levels
- inflammation of hair follicles (folliculitis)
- tiredness

- lower respiratory tract infections
- nausea
- genital yeast infection
- low red blood cell count (anemia)
- low number of certain types of white blood cells (neutropenia)
- stomach-area (abdominal) pain
- shingles (herpes zoster)
- increased weight

These are not all of the possible side effects of OLUMIANT.
Call your doctor for medical advice about side effects. You may report side effects to FDA at 1-800-FDA-1088.

How should I store OLUMIANT?
Store OLUMIANT at room temperature between 68°F to 77°F (20°C to 25°C).
Keep OLUMIANT and all medicines out of the reach of children.

General Information about the safe and effective use of OLUMIANT.
Medicines are sometimes prescribed for purposes other than those listed in a Medication Guide. Do not use OLUMIANT for a condition for which it was not prescribed. Do not give OLUMIANT to other people, even if they have the same symptoms that you have. It may harm them. You can ask your healthcare provider or pharmacist for information about OLUMIANT that is written for health professionals.

What are the ingredients in OLUMIANT?
Active ingredient: baricitinib
Inactive ingredients: croscarmellose sodium, magnesium stearate, mannitol, microcrystalline cellulose, ferric oxide, lecithin (soya), polyethylene glycol, polyvinyl alcohol, talc, titanium dioxide.
OLUMIANT is a registered trademark of Eli Lilly and Company.
Marketed by: Lilly USA, LLC Indianapolis, IN 46285, USA
Copyright © 2018, 2022, Eli Lilly and Company. All rights reserved.
For more information, call 1-800-545-5979 or go to the following website: www.olumiant.com.

This Medication Guide has been approved by the U.S. Food and Drug Administration.

Revised: 06/2022

OLM-0005-MG-20220613

PACKAGE LABEL – OLUMIANT 2 mg 30ct Bottle

Rx Only

Always Dispense with Medication Guide

NDC 0002-4182-30

Olumiant®

(baricitinib) tablets

2 mg

30 tablets

Lilly

PACKAGE LABEL – OLUMIANT 1 mg 30ct Bottle

Rx Only

Always Dispense with Medication Guide

NDC 0002-4732-30

Olumiant®

(baricitinib) tablets

1 mg

30 tablets

Lilly

PACKAGE LABEL – OLUMIANT 4 mg 30ct Bottle

Rx Only

Always Dispense with Medication Guide

NDC 0002-4479-30

Olumiant®

(baricitinib) tablets

4 mg

30 tablets

Lilly